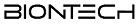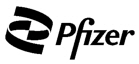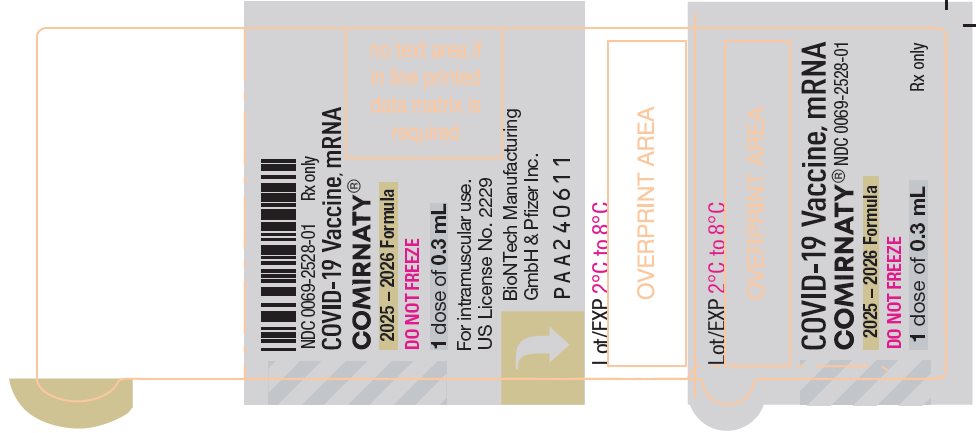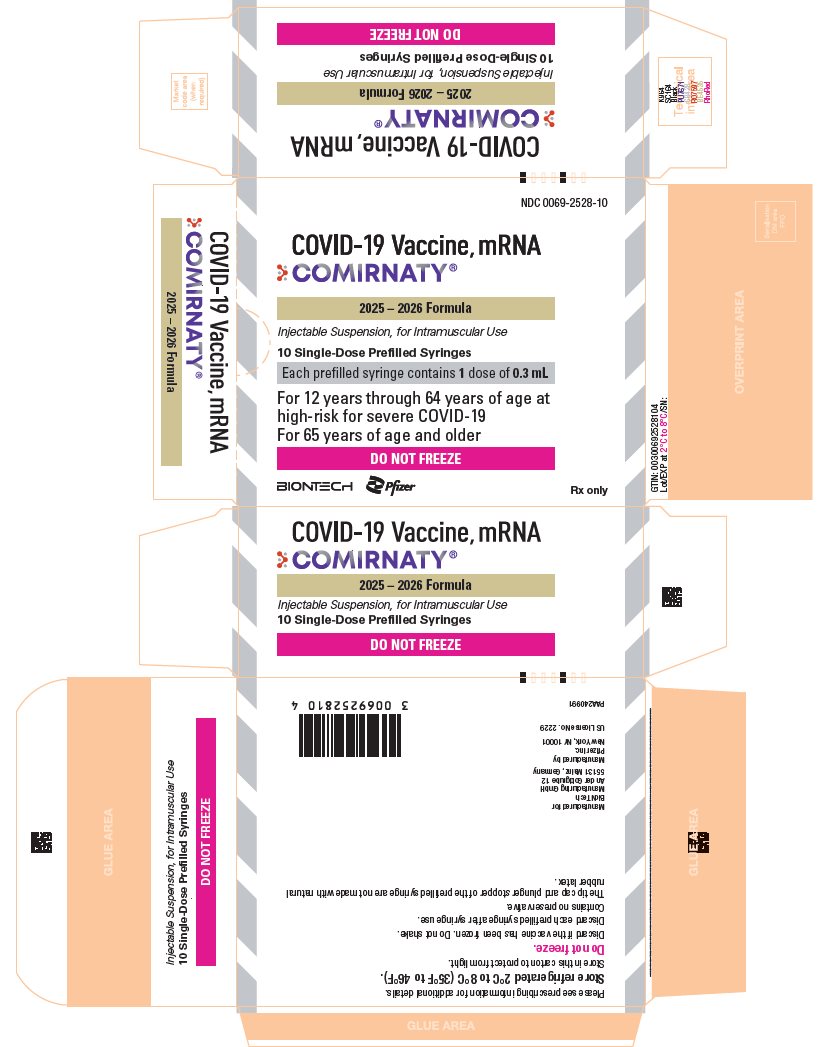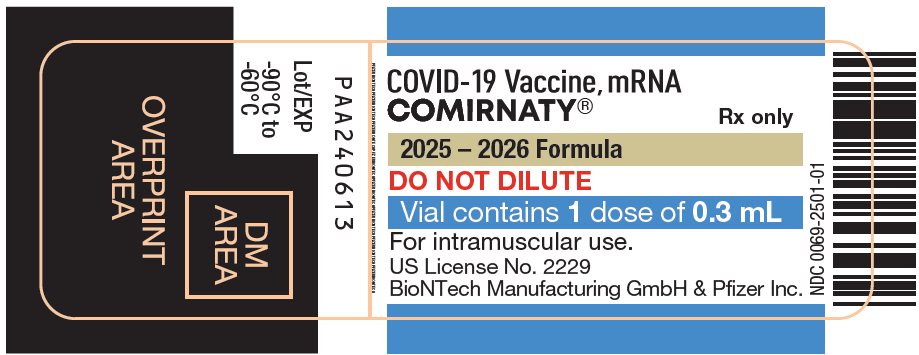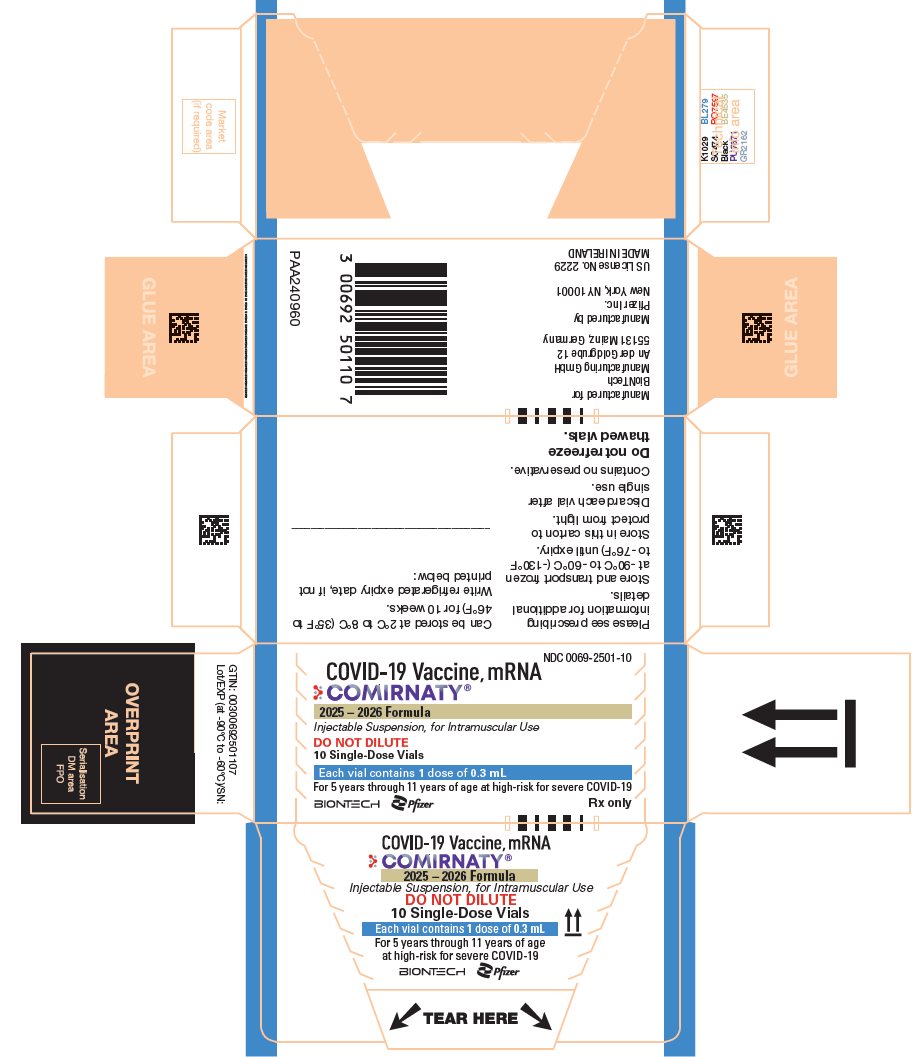 DRUG LABEL: Comirnaty
NDC: 0069-2528 | Form: INJECTION, SUSPENSION
Manufacturer: Pfizer Laboratories Div Pfizer Inc
Category: other | Type: VACCINE LABEL
Date: 20260123

ACTIVE INGREDIENTS: BNT162b2 Omicron (LP.8.1) 0.042 mg/0.418 mL
INACTIVE INGREDIENTS: ((4-HYDROXYBUTYL)AZANEDIYL)BIS(HEXANE-6,1-DIYL)BIS(2-HEXYLDECANOATE) 0.598 mg/0.418 mL; 2-(MPEG 2000)-N,N-DITETRADECYLACETAMIDE 0.075 mg/0.418 mL; 1,2-DISTEAROYL-SN-GLYCERO-3-PHOSPHOCHOLINE 0.130 mg/0.418 mL; CHOLESTEROL 0.259 mg/0.418 mL; SUCROSE 43.1 mg/0.418 mL; TROMETHAMINE 0.084 mg/0.418 mL; TROMETHAMINE HYDROCHLORIDE 0.552 mg/0.418 mL; WATER

HIGHLIGHTS OF PRESCRIBING INFORMATION

These highlights do not include all the information needed to use COMIRNATY safely and effectively. See full prescribing information for COMIRNATY.
COMIRNATY® (COVID-19 Vaccine, mRNA) injectable suspension, for intramuscular use
2025-2026 Formula
Initial U.S. Approval: 2021

RECENT MAJOR CHANGES

Indications and Usage (1) | 8/2025
Dosage and Administration, Preparation for Administration (2.1) | 8/2025
Dosage and Administration, Administration Information (2.2) | 8/2025
Dosage and Administration, Vaccination Schedule (2.3) | 8/2025
Warnings and Precautions, Myocarditis and Pericarditis (5.2) | 6/2025

1 INDICATIONS AND USAGE

COMIRNATY is a vaccine indicated for active immunization to prevent coronavirus disease 2019 (COVID-19) caused by severe acute respiratory syndrome coronavirus 2 (SARS-CoV-2). (1)

COMIRNATY is approved for use in individuals who are:

- 65 years of age and older, or
- 5 years through 64 years of age with at least one underlying condition that puts them at high risk for severe outcomes from COVID-19. (1)

2 DOSAGE AND ADMINISTRATION

For intramuscular use. (2)

- COMIRNATY is administered as a single 0.3 mL dose. (2.2)
- For individuals previously vaccinated with any COVID-19 vaccine, administer the dose of COMIRNATY at least 2 months after the last dose of COVID-19 vaccine. (2.3)

3 DOSAGE FORMS AND STRENGTHS

COMIRNATY is an injectable suspension.

- 5 years through 11 years of age: a single dose is 0.3 mL supplied in vials with blue caps and labeled with blue borders. (3)
- 12 years of age and older: a single dose is 0.3 mL supplied in prefilled syringes labeled with gray borders. (3)

4 CONTRAINDICATIONS

Known history of a severe allergic reaction (e.g., anaphylaxis) to any component of COMIRNATY. (4)

5 WARNINGS AND PRECAUTIONS

- Analyses of postmarketing data from use of authorized or approved mRNA COVID-19 vaccines, including COMIRNATY, have demonstrated increased risks of myocarditis and pericarditis, with onset of symptoms typically in the first week following vaccination. The observed risk has been highest in males 12 years through 24 years of age. (5.2)
- Syncope (fainting) may occur in association with administration of injectable vaccines, including COMIRNATY. Procedures should be in place to avoid injury from fainting. (5.3)

6 ADVERSE REACTIONS

- Participants 12 years of age and older: The most commonly reported adverse reactions (≥10%) after a dose of COMIRNATY were pain at the injection site (up to 90.5%), fatigue (up to 77.5%), headache (up to 75.5%), chills (up to 49.2%), muscle pain (up to 45.5%), joint pain (up to 27.5%), fever (up to 24.3%), injection site swelling (up to 11.8%), and injection site redness (up to 10.4%). (6.1)
- Participants 5 years through 11 years of age: The most commonly reported adverse reactions (≥5%) following any dose were pain at the injection site (up to 83.8%), fatigue (up to 51.9%), headache (up to 38.4%), injection site redness (up to 25.9%), injection site swelling (up to 20.0%), muscle pain (up to 18.1%), chills (up to 13.3%), fever (up to 7.8%), and joint pain (up to 7.6%). (6.1)

To report SUSPECTED ADVERSE REACTIONS, contact Pfizer Inc. at 1-800-438-1985 or VAERS at 1-800-822-7967 or http://vaers.hhs.gov.

FULL PRESCRIBING INFORMATION

1 INDICATIONS AND USAGE

COMIRNATY is a vaccine indicated for active immunization to prevent coronavirus disease 2019 (COVID-19) caused by severe acute respiratory syndrome coronavirus 2 (SARS-CoV-2).

COMIRNATY is approved for use in individuals who are:

- 65 years of age and older, or
- 5 years through 64 years of age with at least one underlying condition that puts them at high risk for severe outcomes from COVID-19.

2 DOSAGE AND ADMINISTRATION

For intramuscular use.

2.1 Preparation for Administration

COMIRNATY Single-Dose Prefilled Syringes for Individuals 65 Years of Age and Older and Individuals 12 Years Through 64 Years of Age with at Least One Underlying Condition that Puts Them at High Risk for Severe Outcomes from COVID-19:

- Verify that the label on the prefilled syringe states 2025-2026 Formula.
- If prefilled syringe has been frozen, discard.
- Do not shake.
- Remove tip cap by slowly turning the cap counterclockwise while holding the Luer lock and attach a sterile needle. Use immediately. If COMIRNATY cannot be used immediately, it must be used within 4 hours.

COMIRNATY Single-Dose Vials for Individuals 5 Years Through 11 Years of Age with at Least One Underlying Condition that Puts Them at High Risk for Severe Outcomes from COVID-19:

- Verify that the label on the vial states 2025-2026 Formula.
- If vial is frozen, thaw vial in the refrigerator [2ºC to 8ºC (35ºF to 46ºF) for up to 2 hours] or at room temperature [up to 25ºC (77ºF) for 30 minutes] [see How Supplied/Storage and Handling (16)].
- Prior to use, mix by inverting vial gently 10 times. Do not shake.
- Withdraw a single 0.3 mL dose using a sterile needle and syringe.
- Discard vial and any excess volume.

2.2 Administration Information

Parenteral drug products should be inspected visually for particulate matter and discoloration prior to administration, whenever solution and container permit. For the prefilled syringe, the vaccine will be a white to off-white suspension and for the vial, the vaccine will be clear to slightly opalescent suspension. Do not administer if vaccine is discolored or contains particulate matter.

Administer the 0.3 mL dose intramuscularly immediately after preparation. For the prefilled syringe, administer the entire volume to deliver a single 0.3 mL dose.

2.3 Vaccination Schedule

COMIRNATY is administered as a single dose for individuals 5 years of age and older.

For individuals previously vaccinated with any COVID-19 vaccine, administer the dose of COMIRNATY at least 2 months after the last dose of COVID-19 vaccine.

3 DOSAGE FORMS AND STRENGTHS

COMIRNATY is an injectable suspension.

- For individuals 5 years through 11 years of age: a single dose is 0.3 mL supplied in vials with blue caps and labeled with blue borders.
- For individuals 12 years of age and older: a single dose is 0.3 mL supplied in prefilled syringes labeled with gray borders.

4 CONTRAINDICATIONS

Do not administer COMIRNATY to individuals with known history of a severe allergic reaction (e.g., anaphylaxis) to any component of COMIRNATY [see Description (11)] or to individuals who had a severe allergic reaction (e.g., anaphylaxis) following a previous dose of a Pfizer-BioNTech COVID-19 vaccine.

5 WARNINGS AND PRECAUTIONS

5.1 Management of Acute Allergic Reactions

Appropriate medical treatment must be immediately available to manage potential anaphylactic reactions following administration of COMIRNATY.

5.2 Myocarditis and Pericarditis

Analyses of postmarketing data from use of authorized or approved mRNA COVID-19 vaccines, including COMIRNATY, have demonstrated increased risks of myocarditis and pericarditis, with onset of symptoms typically in the first week following vaccination. The observed risk has been highest in males 12 years through 24 years of age.

Based on analyses of commercial health insurance claims data from inpatient and outpatient settings, the estimated unadjusted incidence of myocarditis and/or pericarditis during the period 1 through 7 days following administration of the 2023-2024 Formula of mRNA COVID-19 vaccines was approximately 8 cases per million doses in individuals 6 months through 64 years of age and approximately 27 cases per million doses in males 12 through 24 years of age.

Although some individuals with myocarditis and/or pericarditis following administration of mRNA COVID-19 vaccines have required intensive care support, available data suggest that individuals typically have resolution of symptoms within a few days with conservative management.

Follow-up information on cardiovascular outcomes in hospitalized patients who had been diagnosed with COVID-19 vaccine-associated myocarditis is available from a longitudinal retrospective observational study. Most of these patients had received a two-dose primary series of an mRNA COVID-19 vaccine prior to their diagnosis. In this study, at a median follow-up of approximately 5 months post-vaccination, persistence of abnormal cardiac magnetic resonance imaging (CMR) findings that are a marker for myocardial injury was common. The clinical and prognostic significance of these CMR findings is not known^1 [see Adverse Reactions (6.2)].

Information is not yet available about potential long-term sequelae of myocarditis or pericarditis following administration of mRNA COVID-19 vaccines.

The Centers for Disease Control and Prevention (CDC) has published considerations related to myocarditis and pericarditis after vaccination, including for vaccination of individuals with a history of myocarditis or pericarditis (https://www.cdc.gov/vaccines/covid-19/clinical-considerations/myocarditis.html).

5.3 Syncope

Syncope (fainting) may occur in association with administration of injectable vaccines, including COMIRNATY. Procedures should be in place to avoid injury from fainting.

5.4 Altered Immunocompetence

Immunocompromised persons, including individuals receiving immunosuppressant therapy, may have a diminished immune response to COMIRNATY [see Use in Specific Populations (8.6)].

5.5 Limitation of Effectiveness

COMIRNATY may not protect all vaccine recipients.

6 ADVERSE REACTIONS

An overview of clinical studies contributing to the safety assessment of COMIRNATY is provided in Table 1 and Table 2. Participants in these clinical studies received a single dose or a 2-dose series administered 3 weeks apart (referred to as a primary series) and subsequent doses referred to as booster doses.

Table 1: Clinical Studies – Adults and Adolescents 12 Years of Age and Older
Study | Age Group | Vaccine Strain Composition | Dosing | Number of Participants
Primary Series
Study 1; (NCT04380701) | 18 through 55 years of age | Original [COMIRNATY encoding the viral spike (S) glycoprotein of SARS-CoV-2 Wuhan-Hu-1 strain [Original, 30 mcg nucleoside−modified messenger RNA (modRNA)].] | Primary series | 60
Study 2; (NCT04368728) | 16 years of age and older | Original | Primary series | 22,026 [Received COMIRNATY during placebo-control period.]
Study 2; (NCT04368728) | 12 through 15 years of age | Original | Primary series | 1,131
Booster Dose
Study 4; (NCT04955626) | 16 years of age and older | Original | 1st booster | 5,081
Study 2; (NCT04368728) | 18 through 55 years of age | Original | 1st booster | 306
Study 4; (NCT04955626) | 12 through 17 years of age | Original | 1st booster | 65
Study 2; (NCT04368728) | 12 through 15 years of age | Original | 1st booster | 825
Study 5; (NCT05472038) | 12 years of age and older | Original and Omicron BA.4/BA.5 [Vaccine encoding the viral spike (S) glycoprotein of SARS-CoV-2 Wuhan-Hu-1 strain (Original) and Omicron variant lineages BA.4 and BA.5 (Omicron BA.4/BA.5), previously authorized as Pfizer-BioNTech COVID-19 Vaccine, Bivalent (30 mcg modRNA).] | 2nd booster | 726
Concomitant Administration
Study 8; (NCT05310084) | 18 through 64 years of age | Original | 2nd booster administered alone or concomitantly with Influenza Vaccine [Influenza Vaccine (Afluria® Quadrivalent).] | 1,128
Abbreviation: SARS-CoV-2 = severe acute respiratory syndrome coronavirus 2.

Table 2: Clinical Studies – Children 5 Years Through 11 Years of Age
Study | Age Group | Vaccine Strain Composition | Dosing | Number of Participants
Primary Series
Study 3; (NCT04816643) | 5 through 11 years of age | Original [COMIRNATY encoding the viral spike (S) glycoprotein of SARS-CoV-2 Wuhan-Hu-1 strain (Original, 10 mcg modRNA).] | Primary series | 3,109 [Received COMIRNATY during placebo-control period.]
Booster Dose
Study 3; (NCT04816643) | 5 through 11 years of age | Original | 1st booster | 2,408
Study 6; (NCT05543616) | 5 through 11 years of age | Original and Omicron BA.4/BA.5 [Vaccine encoding the viral spike (S) glycoprotein of SARS-CoV-2 Wuhan-Hu-1 strain (Original) and Omicron variant lineages BA.4 and BA.5 (Omicron BA.4/BA.5), previously authorized as Pfizer-BioNTech COVID-19 Vaccine, Bivalent (10 mcg modRNA).] | 2nd booster | 113
Single Dose
Study 6; (NCT05543616) | 5 through 11 years of age | Omicron XBB.1.5 [COMIRNATY encoding the viral spike (S) glycoprotein of SARS-CoV-2 Omicron XBB.1.5 (10 mcg modRNA).] | Single dose | 310
Abbreviation: SARS-CoV-2 = severe acute respiratory syndrome coronavirus 2.

Participants 12 years of age and older: The most commonly reported adverse reactions (≥10%) after a dose of COMIRNATY were pain at the injection site (up to 90.5%), fatigue (up to 77.5%), headache (up to 75.5%), chills (up to 49.2%), muscle pain (up to 45.5%), joint pain (up to 27.5%), fever (up to 24.3%), injection site swelling (up to 11.8%), and injection site redness (up to 10.4%).

Participants 5 years through 11 years of age: The most commonly reported adverse reactions (≥5%) following any dose were pain at the injection site (up to 83.8%), fatigue (up to 51.9%), headache (up to 38.4%), injection site redness (up to 25.9%), injection site swelling (up to 20.0%), muscle pain (up to 18.1%), chills (up to 13.3%), fever (up to 7.8%), and joint pain (up to 7.6%).

6.1 Clinical Trials Experience

Because clinical trials are conducted under widely varying conditions, adverse reaction rates observed in the clinical trials of a vaccine cannot be directly compared to rates in the clinical trials of another vaccine and may not reflect the rates observed in practice.

Adults and Adolescents 12 Years of Age and Older

Two-Dose Series (Original Monovalent) in Vaccine-Naïve Individuals 16 Years of Age and Older

The safety of a 2-dose primary series of COMIRNATY was evaluated in participants 12 years of age and older in 2 clinical studies conducted in Germany (Study 1), United States, Argentina, Brazil, Turkey, South Africa, and Germany (Study 2). Study BNT162-01 (Study 1) was a Phase 1/2, 2-part, dose-escalation trial that enrolled 60 participants, 18 through 55 years of age and 36 participants, 56 through 85 years of age. Study 2 was a Phase 1/2/3 multicenter, randomized, saline placebo-controlled, double-blinded (Phase 2/3), dose-finding, vaccine candidate-selection and efficacy study that enrolled approximately 44,000 participants 16 years of age or older (22,026 COMIRNATY; 22,021 placebo).

Study 2 included 200 participants with confirmed stable human immunodeficiency virus (HIV) infection. Confirmed stable HIV infection was defined as documented viral load <50 copies/mL and CD4 count >200 cells/mm^3 within 6 months before enrollment, and on stable antiretroviral therapy for at least 6 months. HIV-positive participants are included in the safety population but are summarized separately in the safety analyses.

In Study 2, participants 16 years and older in the reactogenicity subset were monitored using an electronic diary for solicited local and systemic reactions and use of antipyretic medication after each vaccination. Participants were also monitored for unsolicited adverse events throughout the study (from Dose 1 through 1 month [all unsolicited adverse events] or through 6 months [serious adverse events] after the last vaccination). Tables 3 and 6 present the frequency and severity of solicited local and systemic reactions, respectively, within 7 days following Dose 1 or Dose 2 of COMIRNATY.

At the time of the analysis of Study 2 with a data cutoff of March 13, 2021, there were 25,651 (58.2%) participants (13,031 COMIRNATY; 12,620 placebo) 16 years of age and older followed for ≥4 months after the second dose.

Demographic characteristics in Study 2 were generally similar with regard to age, sex, race, and ethnicity among participants who received COMIRNATY and those who received placebo. Overall, among the total participants who received either COMIRNATY or placebo, 50.9% were male, 49.1% were female, 79.3% were 16 through 64 years of age, 20.7% were 65 years of age and older, 82.0% were White, 9.6% were Black or African American, 25.9% were Hispanic/Latino, 4.3% were Asian, and 1.0% were American Indian or Alaska Native.

Local and Systemic Solicited Adverse Reactions

In participants 16 through 55 years of age after receiving Dose 2, the mean duration of pain at the injection site was 2.5 days (range 1 to 70 days), for redness 2.2 days (range 1 to 9 days), and for swelling 2.1 days (range 1 to 8 days) for participants in the COMIRNATY group.

In participants 56 years of age and older after receiving Dose 2, the mean duration of pain at the injection site was 2.4 days (range 1 to 36 days), for redness 3.0 days (range 1 to 34 days), and for swelling 2.6 days (range 1 to 34 days) for participants in the COMIRNATY group.

Table 3: Study 2 – Frequency and Percentages of Participants With Solicited Local Reactions, by Maximum Severity, Within 7 Days After Each Dose – Participants 16 Through 55 Years of Age – Reactogenicity Subset of the Safety Population [Randomized participants in the safety analysis population who received at least 1 dose of the study intervention. Participants with chronic, stable HIV infection were excluded.]
 | COMIRNATY [Vaccine encoding the viral spike (S) glycoprotein of SARS-CoV-2 Wuhan-Hu-1 strain (Original).]; Dose 1; N [N = Number of participants reporting at least 1 yes or no response for the specified reaction after the specified dose. The N for each reaction was the same, therefore, this information was included in the column header.] =2899; n [n = Number of participants with the specified reaction.] (%) | Placebo; Dose 1; N=2908; n (%) | COMIRNATY; Dose 2; N=2682; n (%) | Placebo; Dose 2; N=2684; n (%)
Redness [Mild: >2.0 to ≤5.0 cm; Moderate: >5.0 to ≤10.0 cm; Severe: >10.0 cm.]
Any (>2.0 cm) | 156 (5.4) | 28 (1.0) | 151 (5.6) | 18 (0.7)
Mild | 113 (3.9) | 19 (0.7) | 90 (3.4) | 12 (0.4)
Moderate | 36 (1.2) | 6 (0.2) | 50 (1.9) | 6 (0.2)
Severe | 7 (0.2) | 3 (0.1) | 11 (0.4) | 0
Swelling
Any (>2.0 cm) | 184 (6.3) | 16 (0.6) | 183 (6.8) | 5 (0.2)
Mild | 124 (4.3) | 6 (0.2) | 110 (4.1) | 3 (0.1)
Moderate | 54 (1.9) | 8 (0.3) | 66 (2.5) | 2 (0.1)
Severe | 6 (0.2) | 2 (0.1) | 7 (0.3) | 0
Pain at the injection site [Mild: does not interfere with activity; Moderate: interferes with activity; Severe: prevents daily activity.]
Any | 2426 (83.7) | 414 (14.2) | 2101 (78.3) | 312 (11.6)
Mild | 1464 (50.5) | 391 (13.4) | 1274 (47.5) | 284 (10.6)
Moderate | 923 (31.8) | 20 (0.7) | 788 (29.4) | 28 (1.0)
Severe | 39 (1.3) | 3 (0.1) | 39 (1.5) | 0
Notes: Reactions were collected in the electronic diary (e-diary) from Day 1 to Day 7 after vaccination.
No Grade 4 solicited local reactions were reported in participants 16 through 55 years of age.

Table 4: Study 2 – Frequency and Percentages of Participants With Solicited Systemic Reactions, by Maximum Severity, Within 7 Days After Each Dose – Participants 16 Through 55 Years of Age – Reactogenicity Subset of the Safety Population [Randomized participants in the safety analysis population who received at least 1 dose of the study intervention. Participants with chronic, stable HIV infection were excluded.]
 | COMIRNATY [Vaccine encoding the viral spike (S) glycoprotein of SARS-CoV-2 Wuhan-Hu-1 strain (Original).]; Dose 1; N [N = Number of participants reporting at least 1 yes or no response for the specified reaction after the specified dose. The N for each reaction or use of antipyretic or pain medication was the same, therefore, this information was included in the column header.] =2899; n [n = Number of participants with the specified reaction.] (%) |  | Placebo; Dose 1; N=2908; n (%) | COMIRNATY; Dose 2; N=2682; n (%) | Placebo; Dose 2; N=2684; n (%)
Fever
≥38.0℃ | 119 (4.1) |  | 25 (0.9) | 440 (16.4) | 11 (0.4)
≥38.0℃ to 38.4℃ | 86 (3.0) |  | 16 (0.6) | 254 (9.5) | 5 (0.2)
>38.4℃ to 38.9℃ | 25 (0.9) |  | 5 (0.2) | 146 (5.4) | 4 (0.1)
>38.9℃ to 40.0℃ | 8 (0.3) |  | 4 (0.1) | 39 (1.5) | 2 (0.1)
>40.0℃ | 0 |  | 0 | 1 (0.0) | 0
Fatigue [Mild: does not interfere with activity; Moderate: some interference with activity; Severe: prevents daily activity.]
Any | 1431 (49.4) |  | 960 (33.0) | 1649 (61.5) | 614 (22.9)
Mild | 760 (26.2) |  | 570 (19.6) | 558 (20.8) | 317 (11.8)
Moderate | 630 (21.7) |  | 372 (12.8) | 949 (35.4) | 283 (10.5)
Severe | 41 (1.4) |  | 18 (0.6) | 142 (5.3) | 14 (0.5)
Headache
Any | 1262 (43.5) |  | 975 (33.5) | 1448 (54.0) | 652 (24.3)
Mild | 785 (27.1) |  | 633 (21.8) | 699 (26.1) | 404 (15.1)
Moderate | 444 (15.3) |  | 318 (10.9) | 658 (24.5) | 230 (8.6)
Severe | 33 (1.1) |  | 24 (0.8) | 91 (3.4) | 18 (0.7)
Chills
Any | 479 (16.5) |  | 199 (6.8) | 1015 (37.8) | 114 (4.2)
Mild | 338 (11.7) |  | 148 (5.1) | 477 (17.8) | 89 (3.3)
Moderate | 126 (4.3) |  | 49 (1.7) | 469 (17.5) | 23 (0.9)
Severe | 15 (0.5) |  | 2 (0.1) | 69 (2.6) | 2 (0.1)
Vomiting [Mild: 1 to 2 times in 24 hours; Moderate: >2 times in 24 hours; Severe: requires intravenous hydration.]
Any | 34 (1.2) |  | 36 (1.2) | 58 (2.2) | 30 (1.1)
Mild | 29 (1.0) |  | 30 (1.0) | 42 (1.6) | 20 (0.7)
Moderate | 5 (0.2) |  | 5 (0.2) | 12 (0.4) | 10 (0.4)
Severe | 0 |  | 1 (0.0) | 4 (0.1) | 0
Diarrhea [Mild: 2 to 3 loose stools in 24 hours; Moderate: 4 to 5 loose stools in 24 hours; Severe: 6 or more loose stools in 24 hours.]
Any | 309 (10.7) |  | 323 (11.1) | 269 (10.0) | 205 (7.6)
Mild | 251 (8.7) |  | 264 (9.1) | 219 (8.2) | 169 (6.3)
Moderate | 55 (1.9) |  | 58 (2.0) | 44 (1.6) | 35 (1.3)
Severe | 3 (0.1) |  | 1 (0.0) | 6 (0.2) | 1 (0.0)
New or worsened muscle pain
Any | 664 (22.9) |  | 329 (11.3) | 1055 (39.3) | 237 (8.8)
Mild | 353 (12.2) |  | 231 (7.9) | 441 (16.4) | 150 (5.6)
Moderate | 296 (10.2) |  | 96 (3.3) | 552 (20.6) | 84 (3.1)
Severe | 15 (0.5) |  | 2 (0.1) | 62 (2.3) | 3 (0.1)
New or worsened joint pain
Any | 342 (11.8) |  | 168 (5.8) | 638 (23.8) | 147 (5.5)
Mild | 200 (6.9) |  | 112 (3.9) | 291 (10.9) | 82 (3.1)
Moderate | 137 (4.7) |  | 55 (1.9) | 320 (11.9) | 61 (2.3)
Severe | 5 (0.2) |  | 1 (0.0) | 27 (1.0) | 4 (0.1)
Use of antipyretic or pain medication [Severity was not collected for use of antipyretic or pain medication.] | 805 (27.8) |  | 398 (13.7) | 1213 (45.2) | 320 (11.9)
Notes: Reactions and use of antipyretic or pain medication were collected in the electronic diary (e-diary) from Day 1 to Day 7 after each dose.
No Grade 4 solicited systemic reactions were reported in participants 16 through 55 years of age.

Table 5: Study 2 – Frequency and Percentages of Participants With Solicited Local Reactions, by Maximum Severity, Within 7 Days After Each Dose – Participants 56 Years of Age and Older – Reactogenicity Subset of the Safety Population [Randomized participants in the safety analysis population who received at least 1 dose of the study intervention. Participants with chronic, stable HIV infection were excluded.]
 | COMIRNATY [Vaccine encoding the viral spike (S) glycoprotein of SARS-CoV-2 Wuhan-Hu-1 strain (Original).]; Dose 1; N [N = Number of participants reporting at least 1 yes or no response for the specified reaction after the specified dose. The N for each reaction was the same, therefore, the information was included in the column header.] =2008; n [n = Number of participants with the specified reaction.] (%) |  | Placebo; Dose 1; N=1989; n (%) | COMIRNATY; Dose 2; N=1860; n (%) | Placebo; Dose 2; N=1833; n (%)
Redness [Mild: >2.0 to ≤5.0 cm; Moderate: >5.0 to ≤10.0 cm; Severe: >10.0 cm.]
Any (>2.0 cm) | 106 (5.3) |  | 20 (1.0) | 133 (7.2) | 14 (0.8)
Mild | 71 (3.5) |  | 13 (0.7) | 65 (3.5) | 10 (0.5)
Moderate | 30 (1.5) |  | 5 (0.3) | 58 (3.1) | 3 (0.2)
Severe | 5 (0.2) |  | 2 (0.1) | 10 (0.5) | 1 (0.1)
Swelling
Any (>2.0 cm) | 141 (7.0) |  | 23 (1.2) | 145 (7.8) | 13 (0.7)
Mild | 87 (4.3) |  | 11 (0.6) | 80 (4.3) | 5 (0.3)
Moderate | 52 (2.6) |  | 12 (0.6) | 61 (3.3) | 7 (0.4)
Severe | 2 (0.1) |  | 0 | 4 (0.2) | 1 (0.1)
Pain at the injection site [Mild: does not interfere with activity; Moderate: interferes with activity; Severe: prevents daily activity.]
Any (>2.0 cm) | 1408 (70.1) |  | 185 (9.3) | 1230 (66.1) | 143 (7.8)
Mild | 1108 (55.2) |  | 177 (8.9) | 873 (46.9) | 138 (7.5)
Moderate | 296 (14.7) |  | 8 (0.4) | 347 (18.7) | 5 (0.3)
Severe | 4 (0.2) |  | 0 | 10 (0.5) | 0
Notes: Reactions were collected in the electronic diary (e-diary) from Day 1 to Day 7 after vaccination.
No Grade 4 solicited local reactions were reported in participants 56 years of age and older.

Table 6: Study 2 – Frequency and Percentages of Participants With Solicited Systemic Reactions, by Maximum Severity, Within 7 Days After Each Dose – Participants 56 Years of Age and Older – Reactogenicity Subset of the Safety Population [Randomized participants in the safety analysis population who received at least 1 dose of the study intervention. Participants with chronic, stable HIV infection were excluded.]
 | COMIRNATY [Vaccine encoding the viral spike (S) glycoprotein of SARS-CoV-2 Wuhan-Hu-1 strain (Original).]; Dose 1; N [N = Number of participants reporting at least 1 yes or no response for the specified reaction after the specified dose. N for each reaction or use of antipyretic or pain medication was the same, therefore was included in the column header.] =2008; n [n = Number of participants with the specified reaction.] (%) |  | Placebo; Dose 1; N=1989; n (%) | COMIRNATY; Dose 2; N=1860; n (%) | Placebo; Dose 2; N=1833; n (%)
Fever
≥38.0℃ | 26 (1.3) |  | 8 (0.4) | 219 (11.8) | 4 (0.2)
≥38.0℃ to 38.4℃ | 23 (1.1) |  | 3 (0.2) | 158 (8.5) | 2 (0.1)
>38.4℃ to 38.9℃ | 2 (0.1) |  | 3 (0.2) | 54 (2.9) | 1 (0.1)
>38.9℃ to 40.0℃ | 1 (0.0) |  | 2 (0.1) | 7 (0.4) | 1 (0.1)
>40.0℃ | 0 |  | 0 | 0 | 0
Fatigue [Mild: does not interfere with activity; Moderate: some interference with activity; Severe: prevents daily activity; Grade 4 reactions were defined in the clinical study protocol as emergency room visit or hospitalization for severe fatigue, severe headache, severe chills, severe muscle pain, or severe joint pain.]
Any | 677 (33.7) |  | 447 (22.5) | 949 (51.0) | 306 (16.7)
Mild | 415 (20.7) |  | 281 (14.1) | 391 (21.0) | 183 (10.0)
Moderate | 259 (12.9) |  | 163 (8.2) | 497 (26.7) | 121 (6.6)
Severe | 3 (0.1) |  | 3 (0.2) | 60 (3.2) | 2 (0.1)
Grade 4 | 0 |  | 0 | 1 (0.1) | 0
Headache
Any | 503 (25.0) |  | 363 (18.3) | 733 (39.4) | 259 (14.1)
Mild | 381 (19.0) |  | 267 (13.4) | 464 (24.9) | 189 (10.3)
Moderate | 120 (6.0) |  | 93 (4.7) | 256 (13.8) | 65 (3.5)
Severe | 2 (0.1) |  | 3 (0.2) | 13 (0.7) | 5 (0.3)
Chills
Any | 130 (6.5) |  | 69 (3.5) | 435 (23.4) | 57 (3.1)
Mild | 102 (5.1) |  | 49 (2.5) | 229 (12.3) | 45 (2.5)
Moderate | 28 (1.4) |  | 19 (1.0) | 185 (9.9) | 12 (0.7)
Severe | 0 |  | 1 (0.1) | 21 (1.1) | 0
Vomiting [Mild: 1 to 2 times in 24 hours; Moderate: >2 times in 24 hours; Severe: requires intravenous hydration; Grade 4 emergency visit or hospitalization for severe vomiting.]
Any | 10 (0.5) |  | 9 (0.5) | 13 (0.7) | 5 (0.3)
Mild | 9 (0.4) |  | 9 (0.5) | 10 (0.5) | 5 (0.3)
Moderate | 1 (0.0) |  | 0 | 1 (0.1) | 0
Severe | 0 |  | 0 | 2 (0.1) | 0
Diarrhea [Mild: 2 to 3 loose stools in 24 hours; Moderate: 4 to 5 loose stools in 24 hours; Severe: 6 or more loose stools in 24 hours; Grade 4: emergency room or hospitalization for severe diarrhea.]
Any | 168 (8.4) |  | 130 (6.5) | 152 (8.2) | 102 (5.6)
Mild | 137 (6.8) |  | 109 (5.5) | 125 (6.7) | 76 (4.1)
Moderate | 27 (1.3) |  | 20 (1.0) | 25 (1.3) | 22 (1.2)
Severe | 4 (0.2) |  | 1 (0.1) | 2 (0.1) | 4 (0.2)
New or worsened muscle pain
Any | 274 (13.6) |  | 165 (8.3) | 537 (28.9) | 99 (5.4)
Mild | 183 (9.1) |  | 111 (5.6) | 229 (12.3) | 65 (3.5)
Moderate | 90 (4.5) |  | 51 (2.6) | 288 (15.5) | 33 (1.8)
Severe | 1 (0.0) |  | 3 (0.2) | 20 (1.1) | 1 (0.1)
New or worsened joint pain
Any | 175 (8.7) |  | 124 (6.2) | 353 (19.0) | 72 (3.9)
Mild | 119 (5.9) |  | 78 (3.9) | 183 (9.8) | 44 (2.4)
Moderate | 53 (2.6) |  | 45 (2.3) | 161 (8.7) | 27 (1.5)
Severe | 3 (0.1) |  | 1 (0.1) | 9 (0.5) | 1 (0.1)
Use of antipyretic or pain medication [Severity was not collected for use of antipyretic or pain medication.] | 382 (19.0) |  | 224 (11.3) | 688 (37.0) | 170 (9.3)
Notes: Reactions and use of antipyretic or pain medication were collected in the electronic diary (e-diary) from Day 1 to Day 7 after each dose.
The only Grade 4 solicited systemic reaction reported in participants 56 years of age and older was fatigue.

In participants with chronic, stable HIV infection the frequencies of solicited local and systemic adverse reactions were similar to or lower than those observed for all participants 16 years of age and older.

Unsolicited Adverse Events

Overall, 11,253 (51.1%) participants 16 years of age and older in the COMIRNATY group and 11,316 (51.4%) participants in the placebo group had follow-up time between ≥4 months to <6 months after Dose 2 in the blinded placebo-controlled follow-up period with an additional 1,778 (8.1%) and 1,304 (5.9%) with ≥6 months of blinded follow-up time in the COMIRNATY and placebo groups, respectively.

A total of 12,006 (54.5%) participants originally randomized to COMIRNATY had ≥6 months total (blinded and unblinded) follow-up after Dose 2.

In an analysis of all unsolicited adverse events reported following any dose, through 1 month after Dose 2, in participants 16 years of age and older (N = 43,847; 21,926 COMIRNATY group vs. 21,921 placebo group), those assessed as adverse reactions not already captured by solicited local and systemic reactions were nausea (274 vs. 87), malaise (130 vs. 22), lymphadenopathy (83 vs. 7), asthenia (76 vs. 25), decreased appetite (39 vs. 9), hyperhidrosis (31 vs. 9), lethargy (25 vs. 6), and night sweats (17 vs. 3).

In analyses of all unsolicited adverse events in Study 2 from Dose 1 up to the participant unblinding date, 58.2% of study participants had at least 4 months of follow-up after Dose 2. Among participants 16 through 55 years of age who received at least 1 dose of study vaccine, 12,995 of whom received COMIRNATY and 13,026 of whom received placebo, unsolicited adverse events were reported by 4,396 (33.8%) participants in the COMIRNATY group and 2,136 (16.4%) participants in the placebo group. In a similar analysis in participants 56 years of age and older that included 8,931 COMIRNATY recipients and 8,895 placebo recipients, unsolicited adverse events were reported by 2,551 (28.6%) participants in the COMIRNATY group and 1,432 (16.1%) participants in the placebo group. Among participants with confirmed stable HIV infection that included 100 COMIRNATY recipients and 100 placebo recipients, unsolicited adverse events were reported by 29 (29%) participants in the COMIRNATY group and 15 (15%) participants in the placebo group. The higher frequency of reported unsolicited adverse events among COMIRNATY recipients compared to placebo recipients was primarily attributed to events that are consistent with adverse reactions solicited among participants in the reactogenicity subset (Table 5 and Table 6).

Throughout the placebo-controlled safety follow-up period, Bell’s palsy (facial paralysis) was reported by 4 participants in the COMIRNATY group and 2 participants in the placebo group. Onset of facial paralysis was Day 37 after Dose 1 (participant did not receive Dose 2) and Days 3, 9, and 48 after Dose 2. In the placebo group the onset of facial paralysis was Day 32 and Day 102. Currently available information is insufficient to determine a causal relationship with the vaccine. In the analysis of blinded, placebo-controlled follow-up, there were no other notable patterns or numerical imbalances between treatment groups for specific categories of non-serious adverse events (including other neurologic or neuro-inflammatory, and thrombotic events) that would suggest a causal relationship to COMIRNATY. In the analysis of unblinded follow-up, there were no notable patterns of specific categories of non-serious adverse events that would suggest a causal relationship to COMIRNATY.

Serious Adverse Events

Participants 16 through 55 years of age in Study 2 who had received at least 1 dose of vaccine or placebo (COMIRNATY = 12,995; placebo = 13,026), reported serious adverse events from Dose 1 up to the participant unblinding date in ongoing follow-up as follows: 103 (0.8%) COMIRNATY recipients and 117 (0.9%) placebo recipients. In a similar analysis, in participants 56 years of age and older (8,931 COMIRNATY group and 8,895 placebo group), serious adverse events were reported by 165 (1.8%) COMIRNATY recipients and 151 (1.7%) placebo recipients who received at least 1 dose of COMIRNATY or placebo, respectively. In these analyses, 58.2% of study participants had at least 4 months of follow-up after Dose 2. Among participants with confirmed stable HIV infection serious adverse events from Dose 1 up to the participant unblinding date in ongoing follow-up were reported by 2 (2%) COMIRNATY recipients and 2 (2%) placebo recipients.

In the analysis of blinded, placebo-controlled follow-up, there were no notable patterns between treatment groups for specific categories of serious adverse events (including neurologic, neuro-inflammatory, and thrombotic events) that would suggest a causal relationship to COMIRNATY. In the analysis of unblinded follow-up, there were no notable patterns of specific categories of serious adverse events that would suggest a causal relationship to COMIRNATY.

Two-Dose Series (Original Monovalent) in Vaccine-Naïve Adolescents 12 Through 15 Years of Age

Study 2 was a Phase 1/2/3 multicenter, randomized, saline placebo-controlled, double-blinded (Phase 2/3), dose-finding, vaccine candidate-selection and efficacy study. In Study 2, 2,260 adolescents (1,131 COMIRNATY; 1,129 placebo) were 12 through 15 years of age. At the time of the analysis of the ongoing Study 2 with a data cutoff of September 2, 2021, there were 1,559 (69.0%) adolescents (786 COMIRNATY and 773 placebo) 12 through 15 years of age followed for ≥4 months after the second dose.

Demographic characteristics in Study 2 were generally similar with regard to age, sex, race, and ethnicity among adolescents who received COMIRNATY and those who received placebo. Overall, among the adolescents who received COMIRNATY, 50.1% were male and 49.9% were female, 85.8% were White, 4.6% were Black or African American, 11.7% were Hispanic/Latino, 6.4% were Asian, and 0.4% were American Indian/Alaska Native.

In Study 2, participants 12 through 15 years of age in the reactogenicity subset were monitored using an electronic diary for solicited local and systemic reactions and use of antipyretic medication after each vaccination. Participants were also monitored for unsolicited adverse events throughout the study (from Dose 1 through 1 month [all unsolicited adverse events] or through 6 months [serious adverse events] after the last vaccination). Tables 7 through 8 present the frequency and severity of solicited local and systemic reactions, respectively, within 7 days following Dose 1 or Dose 2 of COMIRNATY.

Local and Systemic Solicited Adverse Reactions

In adolescents 12 through 15 years of age after receiving Dose 2, the mean duration of pain at the injection site was 2.5 days (range 1 to 11 days), for redness 1.8 days (range 1 to 5 days), and for swelling 1.6 days (range 1 to 5 days) in the COMIRNATY group.

Table 7: Study 2 – Frequency and Percentages of Adolescents With Solicited Local Reactions, by Maximum Severity, Within 7 Days After Each Dose – Adolescents 12 Through 15 Years of Age – Safety Population [Randomized participants in the safety analysis population who received at least 1 dose of the study intervention.]
 | COMIRNATY [Vaccine encoding the viral spike (S) glycoprotein of SARS-CoV-2 Wuhan-Hu-1 strain (Original).]; Dose 1; N [N = Number of participants reporting at least 1 yes or no response for the specified reaction after the specified dose.] =1127; n [n = Number of participants with the specified reaction.] (%) |  | Placebo; Dose 1; N=1127; n (%) | COMIRNATY; Dose 2; N=1097; n (%) | Placebo; Dose 2; N=1078; n (%)
Redness [Mild: >2.0 to ≤5.0 cm; Moderate: >5.0 to ≤10.0 cm; Severe: >10.0 cm.]
Any (>2 cm) | 65 (5.8) |  | 12 (1.1) | 55 (5.0) | 10 (0.9)
Mild | 44 (3.9) |  | 11 (1.0) | 29 (2.6) | 8 (0.7)
Moderate | 20 (1.8) |  | 1 (0.1) | 26 (2.4) | 2 (0.2)
Severe | 1 (0.1) |  | 0 (0.0) | 0 (0.0) | 0 (0.0)
Swelling
Any (>2 cm) | 78 (6.9) |  | 11 (1.0) | 54 (4.9) | 6 (0.6)
Mild | 55 (4.9) |  | 9 (0.8) | 36 (3.3) | 4 (0.4)
Moderate | 23 (2.0) |  | 2 (0.2) | 18 (1.6) | 2 (0.2)
Severe | 0 (0.0) |  | 0 (0.0) | 0 (0.0) | 0 (0.0)
Pain at the injection site [Mild: does not interfere with activity; Moderate: interferes with activity; Severe: prevents daily activity.]
Any | 971 (86.2) |  | 263 (23.3) | 866 (78.9) | 193 (17.9)
Mild | 467 (41.4) |  | 227 (20.1) | 466 (42.5) | 164 (15.2)
Moderate | 493 (43.7) |  | 36 (3.2) | 393 (35.8) | 29 (2.7)
Severe | 11 (1.0) |  | 0 (0.0) | 7 (0.6) | 0 (0.0)
Note: Reactions were collected in the electronic diary (e-diary) from Day 1 to Day 7 after vaccination.

Table 8: Study 2 – Frequency and Percentages of Adolescents With Solicited Systemic Reactions, by Maximum Severity, Within 7 Days After Each Dose – Adolescents 12 Through 15 Years of Age – Safety Population [Randomized participants in the safety analysis population who received at least 1 dose of the study intervention.]
 | COMIRNATY [Vaccine encoding the viral spike (S) glycoprotein of SARS-CoV-2 Wuhan-Hu-1 strain (Original).]; Dose 1; N [N = Number of participants reporting at least 1 yes or no response for the specified event after the specified dose.] =1127; n [n = Number of participants with the specified reaction.] (%) |  | Placebo; Dose 1; N=1127; n (%) | COMIRNATY; Dose 2; N=1097; n (%) | Placebo; Dose 2; N=1078; n (%)
Fever
≥38.0℃ | 114 (10.1) |  | 12 (1.1) | 215 (19.6) | 7 (0.6)
≥38.0℃ to 38.4℃ | 74 (6.6) |  | 8 (0.7) | 107 (9.8) | 5 (0.5)
>38.4℃ to 38.9℃ | 29 (2.6) |  | 2 (0.2) | 83 (7.6) | 1 (0.1)
>38.9℃ to 40.0℃ | 10 (0.9) |  | 2 (0.2) | 25 (2.3) | 1 (0.1)
>40.0℃ | 1 (0.1) |  | 0 (0.0) | 0 (0.0) | 0 (0.0)
Fatigue [Mild: does not interfere with activity; Moderate: some interference with activity; Severe: prevents daily activity.]
Any | 677 (60.1) |  | 457 (40.6) | 726 (66.2) | 264 (24.5)
Mild | 278 (24.7) |  | 250 (22.2) | 232 (21.1) | 133 (12.3)
Moderate | 384 (34.1) |  | 199 (17.7) | 468 (42.7) | 127 (11.8)
Severe | 15 (1.3) |  | 8 (0.7) | 26 (2.4) | 4 (0.4)
Headache
Any | 623 (55.3) |  | 396 (35.1) | 708 (64.5) | 264 (24.5)
Mild | 361 (32.0) |  | 256 (22.7) | 302 (27.5) | 170 (15.8)
Moderate | 251 (22.3) |  | 131 (11.6) | 384 (35.0) | 93 (8.6)
Severe | 11 (1.0) |  | 9 (0.8) | 22 (2.0) | 1 (0.1)
Chills
Any | 311 (27.6) |  | 109 (9.7) | 455 (41.5) | 74 (6.9)
Mild | 195 (17.3) |  | 82 (7.3) | 221 (20.1) | 53 (4.9)
Moderate | 111 (9.8) |  | 25 (2.2) | 214 (19.5) | 21 (1.9)
Severe | 5 (0.4) |  | 2 (0.2) | 20 (1.8) | 0 (0.0)
Vomiting [Mild: 1 to 2 times in 24 hours; Moderate: >2 times in 24 hours; Severe: requires intravenous hydration.]
Any | 31 (2.8) |  | 10 (0.9) | 29 (2.6) | 12 (1.1)
Mild | 30 (2.7) |  | 8 (0.7) | 25 (2.3) | 11 (1.0)
Moderate | 0 (0.0) |  | 2 (0.2) | 4 (0.4) | 1 (0.1)
Severe | 1 (0.1) |  | 0 (0.0) | 0 (0.0) | 0 (0.0)
Diarrhea [Mild: 2 to 3 loose stools in 24 hours; Moderate: 4 to 5 loose stools in 24 hours; Severe: 6 or more loose stools in 24 hours.]
Any | 90 (8.0) |  | 82 (7.3) | 65 (5.9) | 44 (4.1)
Mild | 77 (6.8) |  | 72 (6.4) | 59 (5.4) | 39 (3.6)
Moderate | 13 (1.2) |  | 10 (0.9) | 6 (0.5) | 5 (0.5)
Severe | 0 (0.0) |  | 0 (0.0) | 0 (0.0) | 0 (0.0)
New or worsened muscle pain
Any | 272 (24.1) |  | 148 (13.1) | 355 (32.4) | 90 (8.3)
Mild | 125 (11.1) |  | 88 (7.8) | 152 (13.9) | 51 (4.7)
Moderate | 145 (12.9) |  | 60 (5.3) | 197 (18.0) | 37 (3.4)
Severe | 2 (0.2) |  | 0 (0.0) | 6 (0.5) | 2 (0.2)
New or worsened joint pain
Any | 109 (9.7) |  | 77 (6.8) | 173 (15.8) | 51 (4.7)
Mild | 66 (5.9) |  | 50 (4.4) | 91 (8.3) | 30 (2.8)
Moderate | 42 (3.7) |  | 27 (2.4) | 78 (7.1) | 21 (1.9)
Severe | 1 (0.1) |  | 0 (0.0) | 4 (0.4) | 0 (0.0)
Use of antipyretic or pain medication [Severity was not collected for use of antipyretic or pain medication.] | 413 (36.6) |  | 111 (9.8) | 557 (50.8) | 95 (8.8)
Note: Events and use of antipyretic or pain medication were collected in the electronic diary (e-diary) from Day 1 to Day 7 after each dose.

Unsolicited Adverse Events

In Study 2, 2,260 adolescents (1,131 COMIRNATY; 1,129 placebo) were 12 through 15 years of age. Of these, 634 (56.1%) participants in the COMIRNATY group and 629 (55.7%) participants in the placebo group had follow-up time between ≥4 months to <6 months after Dose 2 in the blinded placebo-controlled follow-up period with an additional 152 (13.4%) and 144 (12.8%) with ≥6 months of blinded follow-up time in the COMIRNATY and placebo groups, respectively.

A total of 1,113 (98.4%) participants 12 through 15 years of age originally randomized to COMIRNATY had ≥6 months total (blinded and unblinded) follow-up after Dose 2. An analysis of all unsolicited adverse events in Study 2 from Dose 1 up to the participant unblinding date was conducted. Among participants 12 through 15 years of age who received at least 1 dose of study vaccine, unsolicited adverse events were reported by 95 (8.4%) participants in the COMIRNATY group and 113 (10.0%) participants in the placebo group.

In an analysis of all unsolicited adverse events reported during blinded follow-up from Dose 1 through 1 month after Dose 2, in adolescents 12 to 15 years of age, those assessed as adverse reactions not already captured by solicited local and systemic reactions were lymphadenopathy (9 vs. 2), and nausea (5 vs. 2).

In the analysis of blinded, placebo-controlled follow-up, there were no other notable patterns or numerical imbalances between treatment groups for specific categories of unsolicited adverse events (including other neurologic or neuro-inflammatory, and thrombotic events) that would suggest a causal relationship to COMIRNATY. In the analysis of unblinded follow-up, there were no notable patterns of specific categories of non-serious adverse events that would suggest a causal relationship to COMIRNATY.

Serious Adverse Events

In Study 2, among participants 12 through 15 years of age who had received at least 1 dose of vaccine or placebo (COMIRNATY = 1,131; placebo = 1,129), serious adverse events from Dose 1 up to the participant unblinding date in ongoing follow-up were reported by 10 (0.9%) COMIRNATY recipients and 2 (0.2%) placebo recipients. In these analyses, 69.0% of study participants had at least 4 months of follow-up after Dose 2. In the analysis of blinded, placebo-controlled follow-up, there were no notable patterns between treatment groups for specific categories of serious adverse events (including neurologic, neuro-inflammatory, and thrombotic events) that would suggest a causal relationship to COMIRNATY. In the analysis of unblinded follow-up, there were no notable patterns of specific categories of serious adverse events that would suggest a causal relationship to COMIRNATY.

Single Dose (Original Monovalent) in Vaccine-Experienced Individuals 12 Years of Age and Older

16 Years of Age and Older

In Study 4, a double-blind placebo-controlled booster study, 5,081 participants 16 years of age and older recruited from Study 2 received a booster dose of COMIRNATY 10.8 months (median time, range of 5.0 to 12.6 months) after completing the primary series of COMIRNATY series and had a median follow-up time of 2.9 months based on data up to the cutoff date of February 8, 2022. The median age of participants who received COMIRNATY or placebo was 53.0 years (range 16 through 87 years of age), 49.1% were male and 50.9% were female, 79.0% were White, 14.9% were Hispanic/Latino, 9.2% were Black or African American, 5.5% were Asian, and 1.7% were American Indian/Alaska Native.

Adverse reactions reported in participants receiving a booster dose of COMIRNATY were similar to those previously observed in participants receiving COMIRNATY as part of the primary series. Lymphadenopathy occurred in 141 (2.8%) participants who received a booster dose of COMIRNATY and in 83 (0.4%) participants who received COMIRNATY as a primary series.

18 Years Through 55 Years of Age

A subset of 306 Study 2 Phase 2/3 participants 18 through 55 years of age received a booster dose of COMIRNATY 6.8 months (median time, range 4.8 to 8.0 months) after completing the primary series. These participants had a median follow-up time of 8.3 months up to a data cutoff date of November 22, 2021. Among the 306 participants, the median age was 42 years (range 19 through 55 years of age), 45.8% were male and 54.2% were female, 81.4% were White, 27.8% were Hispanic/Latino, 9.2% were Black or African American, 5.2% were Asian, and 0.7% were American Indian/Alaska Native.

Adverse reactions reported in participants receiving a booster dose of COMIRNATY were similar to those previously observed in participants receiving COMIRNATY as part of the primary series. Lymphadenopathy occurred in 16 (5.2%) of participants who received a booster dose of COMIRNATY and 83 (0.4%) in participants who received COMIRNATY as a primary series.

12 Years Through 17 Years of Age

A subset of 65 Study 4 participants 12 through 17 years of age received a booster dose of COMIRNATY 13.3 months (median time, range 6.5 to 16.9 months) after completing the primary series and had a median follow-up time of 5.6 months up to a data cutoff date of July 14, 2022. The median age of participants was 14 years (range 12 through 17 years of age), 49.2% were male and 50.8% were female, 76.9% were White, 16.9% were Hispanic/Latino, 13.8% were Black or African American, 7.7% were Asian, and 1.5% were American Indian/Alaska Native.

Adverse reactions reported in participants receiving a booster dose of COMIRNATY were similar to those previously observed in participants receiving COMIRNATY as part of the primary series. There were no cases of lymphadenopathy reported in participants who received a booster dose of COMIRNATY.

12 Years Through 15 Years of Age

A subset of 825 Study 2 Phase 2/3 participants 12 through 15 years of age received a booster dose of COMIRNATY 11.2 months (median time, range 6.3 to 20.1 months) after completing the primary series and had a median follow-up time of 9.5 months up to a data cutoff date of November 3, 2022. The median age of participants was 14.0 years (range 13 through 15 years of age), 49.3% were male and 50.7% were female, 83.5% were White, 10.8% were Hispanic/Latino, 4.6% were Black or African American, 7.5% were Asian, and 0.4% were American Indian/Alaska Native.

Adverse reactions reported in participants receiving a booster dose of COMIRNATY were similar to those previously observed in participants receiving COMIRNATY as part of the primary series. Lymphadenopathy occurred in 8 (1.0%) participants who received a booster dose of COMIRNATY and in 9 (0.8%) participants who received COMIRNATY as a primary series.

Single Dose (Bivalent Original and BA.4/BA.5) in Vaccine-Experienced Individuals 12 Years of Age and Older

A subset of 107 Study 5 Phase 2/3 participants 12 through 17 years of age, 313 participants 18 through 55 years of age and 306 participants 56 years of age and older previously vaccinated with a 2-dose primary series and 1 booster dose of COMIRNATY, went on to receive a second booster dose with Pfizer-BioNTech COVID-19 Vaccine, Bivalent.

Participants received a second booster dose 11.1 months (median time; range 5.4 to 16.9 months) after receiving the first booster dose and had a median follow-up time of 1.5 months up to a data cutoff date of October 31, 2022. The median age was 48.0 years, 42.7% were male, 57.3% were female, 80.6% were White, 11.4% were Hispanic/Latino, 5.9% were Asian, and 11.4% were Black or African American.

Local and Systemic Solicited Adverse Reactions

Table 9 and Table 10 present the frequency and severity of reported solicited local reactions and systemic reactions, respectively, within 7 days of a second booster dose of Pfizer-BioNTech COVID-19 Vaccine, Bivalent.

In participants 12 years of age and older who received a second booster dose, the mean duration of injection site pain was 2.1 to 2.4 days (range 1 to 11 days), injection site redness was 1.5 to 2.5 days (range 1 to 4 days), and injection site swelling was 1.3 to 1.9 days (range 1 to 4 days), respectively.

Table 9: Study 5 – Frequency and Percentages of Participants With Solicited Local Reactions, by Maximum Severity, Within 7 Days After a Second Booster Dose – Participants 12 Years of Age and Older – Safety Population
 | Pfizer-BioNTech COVID-19 Vaccine, Bivalent [Vaccine encoding the viral spike (S) glycoprotein of SARS-CoV-2 Wuhan-Hu-1 strain (Original) and Omicron variant lineages BA.4 and BA.5 (Omicron BA.4/BA.5).]
 | 12 Through 17 Years of Age; N [N = Number of participants reporting at least 1 yes or no response for the specified reaction after the study vaccination.] =107; n [n = Number of participants with the specified adverse reaction.] (%) | 18 Through 55 Years of Age; N=309 [N = 310 for redness and pain at injection site in participants 18 through 55 years of age; N = 301 for pain at injection site in participants 56 years of age and older.]; n (%) | 56 Years of Age and Older; N=300; n (%)
Redness [Mild: >2.0 to 5.0 cm; Moderate: >5.0 to 10.0 cm; Severe: >10.0 cm.]
Any (>2 cm) | 6 (5.6) | 21 (6.8%) | 11 (3.7%)
Mild | 4 (3.7) | 16 (5.2%) | 7 (2.3)
Moderate | 2 (1.9) | 5 (1.6) | 4 (1.3%)
Severe | 0 | 0 | 0
Swelling
Any (>2 cm) | 8 (7.5) | 23 (7.4%) | 8 (2.7)
Mild | 6 (5.6) | 19 (6.1%) | 5 (1.7)
Moderate | 2 (1.9) | 4 (1.3) | 3 (1.0)
Severe | 0 | 0 | 0
Pain at the injection site [Mild: does not interfere with activity; Moderate: interferes with activity; Severe: prevents daily activity.]
Any | 75 (70.1) | 236 (76.1) | 172 (57.1)
Mild | 45 (42.1) | 178 (57.4) | 147 (48.8)
Moderate | 29 (27.1) | 58 (18.7) | 24 (8.0)
Severe | 1 (0.9) | 0 | 1 (0.3)
Note: Adverse Reactions were collected in the electronic diary (e-diary) from day of vaccination (Day 1) through Day 7 after the study vaccination.

Table 10: Study 5 – Frequency and Percentages of Participants With Solicited Systemic Adverse Reactions, by Maximum Severity, Within 7 Days After a Second Booster Dose – Participants 12 Years of Age and Older – Safety Population
 | Pfizer-BioNTech COVID-19 Vaccine, Bivalent [Vaccine encoding the viral spike (S) glycoprotein of SARS-CoV-2 Wuhan-Hu-1 strain (Original) and Omicron variant lineages BA.4 and BA.5 (Omicron BA.4/BA.5).]
 | 12 Through 17 Years of Age; N [N = Number of participants reporting at least 1 yes or no response for the specified adverse reaction after the study vaccination.] =107; n [n = Number of participants with the specified adverse reaction.] (%) | 18 Through 55 Years of Age; N=309; n (%) | 56 Years of Age and Older; N=300 [N = 301 for fever, fatigue and diarrhea in participants 56 years of age and older.]; n (%)
Fever
≥38.0℃ | 10 (9.3) | 15 (4.9) | 14 (4.7)
≥38.0℃ to 38.4℃ | 7 (6.5) | 9 (2.9) | 10 (3.3)
>38.4℃ to 38.9℃ | 2 (1.9) | 6 (1.9) | 3 (1.0)
>38.9℃ to 40.0℃ | 1 (0.9) | 0 | 0
>40.0℃ | 0 | 0 | 0
Fatigue [Mild: does not interfere with activity; Moderate: some interference with activity; Severe: prevents daily activity.]
Any | 72 (67.3) | 189 (61.2) | 116 (38.5)
Mild | 27 (25.2) | 83 (26.9) | 56 (18.6)
Moderate | 45 (42.1) | 100 (32.4) | 56 (18.6)
Severe | 0 | 6 (1.9) | 4 (1.3)
Headache
Any | 54 (50.5) | 144 (46.6) | 92 (30.7)
Mild | 28 (26.2) | 87 (28.2) | 62 (20.7)
Moderate | 26 (24.3) | 55 (17.8) | 30 (10.0)
Severe | 0 | 2 (0.6) | 0
Chills
Any | 25 (23.4) | 68 (22.0) | 36 (12.0)
Mild | 19 (17.8) | 38 (12.3) | 21 (7.0)
Moderate | 6 (5.6) | 28 (9.1) | 14 (4.7)
Severe | 0 | 2 (0.6) | 1 (0.3)
Vomiting [Mild: 1 to 2 times in 24 hours; Moderate: >2 times in 24 hours; Severe: requires intravenous hydration.]
Any | 3 (2.8) | 6 (1.9) | 2 (0.7)
Mild | 3 (2.8) | 5 (1.6) | 2 (0.7)
Moderate | 0 | 1 (0.3) | 0
Severe | 0 | 0 | 0
Diarrhea [Mild: 2 to 3 loose stools in 24 hours; Moderate: 4 to 5 loose stools in 24 hours; Severe: 6 or more loose stools in 24 hours.]
Any | 7 (6.5) | 33 (10.7) | 29 (9.6)
Mild | 7 (6.5) | 27 (8.7) | 23 (7.6)
Moderate | 0 | 5 (1.6) | 6 (2.0)
Severe | 0 | 1 (0.3) | 0
New or worsened muscle pain
Any | 28 (26.2) | 94 (30.4) | 54 (18.0)
Mild | 12 (11.2) | 47 (15.2) | 30 (10.0)
Moderate | 16 (15.0) | 47 (15.2) | 24 (8.0)
Severe | 0 | 0 | 0
New or worsened joint pain
Any | 13 (12.1) | 46 (14.9) | 36 (12.0)
Mild | 9 (8.4) | 21 (6.8) | 20 (6.7)
Moderate | 4 (3.7) | 25 (8.1) | 16 (5.3)
Severe | 0 | 0 | 0
Use of antipyretic or pain medication [Severity was not collected for use of antipyretic or pain medication.] | 36 (33.6) | 105 (34.0) | 74 (24.7)
Note: Adverse reactions and use of antipyretic or pain medication were collected in the electronic diary (e-diary) from day of vaccination (Day 1) through Day 7 after the study vaccination.

Unsolicited Adverse Events

Among participants 12 years of age and older, unsolicited adverse events were reported by 48 (6.6%) participants who received a second booster dose through 1 month after the booster dose. Lymphadenopathy occurred in 7 (1.0%) participants.

Concomitant Administration of COMIRNATY (Original Monovalent) With Influenza Vaccine in Adults 18 Years Through 64 Years of Age

In Study 8, a Phase 3 study, participants 18 through 64 years of age who received COMIRNATY concomitantly administered with Influenza Vaccine (Afluria Quadrivalent) followed 1 month later by saline placebo (n = 564) were compared to participants who received influenza vaccine with saline placebo followed 1 month later by COMIRNATY (n = 564).

Demographic characteristics in Study 8 among the participants in the concomitant administration and separate administration groups were similar with regard to age, sex, race, and ethnicity. Among the 564 participants in the concomitant administration group, the median age was 39.0 years (range 18 through 64 years of age), 36.9% were male and 63.1% were female, 79.1% were White, 12.9% were Asian, and 0.9% were Hispanic/Latino.

Solicited local and systemic adverse reactions were reported more frequently by participants who received COMIRNATY concomitantly with influenza vaccine, compared to participants who received COMIRNATY alone. The most common adverse reactions reported in the concomitant administration group and after COMIRNATY alone were injection site pain (COMIRNATY injection site) (86.2% and 84.4%, respectively), fatigue (64.0% and 50.8%, respectively), and headache (47.2% and 37.8%, respectively).

Children 5 Years Through 11 Years of Age

Two-Dose Series (Original Monovalent) in Vaccine-Naïve Children 5 Years Through 11 Years of Age

Study 3 is a Phase 1/2/3 multicenter, randomized, dose-finding, open label (Phase 1) and multinational, placebo controlled (saline placebo), observer-blind, immunogenicity and efficacy (Phase 2/3) study that has evaluated 4,695 participants 5 through 11 years of age, of whom 3,109 participants received COMIRNATY and 1,538 participants received placebo in Phase 2/3.

Demographic characteristics were generally similar with regard to age, sex, race, and ethnicity among participants who received COMIRNATY and those who received placebo. Overall, among the 4,647 participants who received at least 1 dose of COMIRNATY or placebo, 51.4% were male and 48.6% were female, 77.5% were White, 6.0% were Black or African American, 17.0% were Hispanic/Latino, 8.1% were Asian, and 0.4% were American Indian/Alaska Native.

In an analysis of Study 3 (Phase 2/3), 4,632 participants 5 through 11 years of age who received a 2-dose primary series [3,100 COMIRNATY; 1,532 placebo] have been followed a median of 1.9 months (range 0.1 to 7.5 months) after the second dose in the blinded placebo-controlled follow-up period up to the cutoff date of May 20, 2022.

In Study 3, participants 5 years through 11 years of age in the reactogenicity subset were monitored using an electronic diary for solicited local and systemic adverse reactions and use of antipyretic medication after each vaccination. Participants were also monitored for unsolicited adverse events throughout the study (from Dose 1 through 1 month [all unsolicited adverse events] or through 6 months [serious adverse events] after the last vaccination). Tables 11 through 12 present the frequency and severity of solicited local and systemic reactions, respectively, within 7 days following Dose 1 or Dose 2 of COMIRNATY.

Solicited Local and Systemic Adverse Reactions

The mean duration of pain at the injection site after Dose 2 was 2.3 days (range 1 to 37 days), for redness 2.0 days (range 1 to 10 days), and for swelling 2.2 days (range 1 to 16 days) for children in the COMIRNATY group in the blinded placebo-controlled follow-up period up to the cutoff date of May 20, 2022.

Table 11: Study 3 – Frequency and Percentages of Participants With Solicited Local Reactions, by Maximum Severity, Within 7 Days After Each Dose – Children 5 Through 11 Years of Age – Safety Population [Randomized participants who received at least 1 dose of the study intervention.]
 | COMIRNATY [Vaccine encoding the viral spike (S) glycoprotein of SARS-CoV-2 Wuhan-Hu-1 strain (Original).]; Dose 1; N [N = Number of participants reporting at least 1 yes or no response for the specified reaction after the specified dose.] =3096; n [n = Number of participants with the specified reaction.] (%) |  | Placebo; Dose 1; N=1531 to 1532; n (%) | COMIRNATY; Dose 2; N=3064; n (%) | Placebo; Dose 2; N=1521 to 1522; n (%)
Redness [Mild: ≥0.5 to <2.0 cm; Moderate: >2.0 to <7.0 cm; Severe: >7.0 cm.]
Any (≥0.5 cm) | 434 (14.0) |  | 91 (5.9) | 575 (18.8) | 79 (5.2)
Mild | 287 (9.3) |  | 78 (5.1) | 315 (10.3) | 57 (3.7)
Moderate | 146 (4.7) |  | 11 (0.7) | 257 (8.4) | 20 (1.3)
Severe | 1 (0.0) |  | 2 (0.1) | 3 (0.1) | 2 (0.1)
Swelling
Any (≥0.5 cm) | 320 (10.3) |  | 46 (3.0) | 450 (14.7) | 41 (2.7)
Mild | 177 (5.7) |  | 28 (1.8) | 247 (8.1) | 30 (2.0)
Moderate | 142 (4.6) |  | 18 (1.2) | 203 (6.6) | 11 (0.7)
Severe | 1 (0.0) |  | 0 | 0 | 0
Pain at the injection site [Mild: does not interfere with activity; Moderate: interferes with activity; Severe: prevents daily activity.]
Any | 2258 (72.9) |  | 482 (31.5) | 2181 (71.2) | 434 (28.5)
Mild | 1810 (58.5) |  | 434 (28.3) | 1642 (53.6) | 389 (25.6)
Moderate | 442 (14.3) |  | 48 (3.1) | 533 (17.4) | 44 (2.9)
Severe | 6 (0.2) |  | 0 | 6 (0.2) | 1 (0.1)
Note: Reactions were collected in an electronic diary (e-diary) from Day 1 to Day 7 after vaccination.

Table 12: Study 3 – Frequency and Percentages of Participants With Solicited Systemic Reactions, by Maximum Severity, Within 7 Days After Each Dose – Children 5 Through 11 Years of Age – Safety Population [Randomized participants who received at least 1 dose of the study intervention.]
 | COMIRNATY [Vaccine encoding the viral spike (S) glycoprotein of SARS-CoV-2 Wuhan-Hu-1 strain (Original).]; Dose 1; N [N = Number of participants reporting at least 1 yes or no response for the specified event after the specified dose.] =3096; n [n = Number of participants with the specified reaction.] (%) |  | Placebo; Dose 1; N=1531 to 1532; n (%) | COMIRNATY; Dose 2; N=3064; n (%) | Placebo; Dose 2; N=1521 to 1522; n (%)
Fever
≥38.0℃ | 64 (2.1) |  | 21 (1.4) | 193 (6.3) | 21 (1.4)
≥38.0℃ to 38.4℃ | 37 (1.2) |  | 10 (0.7) | 101 (3.3) | 13 (0.9)
>38.4℃ to 38.9℃ | 22 (0.7) |  | 9 (0.6) | 70 (2.3) | 5 (0.3)
>38.9℃ to 40.0℃ | 4 (0.1) |  | 2 (0.1) | 21 (0.7) | 3 (0.2)
>40.0℃ | 1 (0.0) |  | 0 | 1 (0.0) | 0
Fatigue [Mild: does not interfere with activity; Moderate: some interference with activity; Severe: prevents daily activity.]
Any | 1067 (34.5) |  | 496 (32.4) | 1200 (39.2) | 383 (25.2)
Mild | 702 (22.7) |  | 323 (21.1) | 665 (21.7) | 230 (15.1)
Moderate | 360 (11.6) |  | 171 (11.2) | 508 (16.6) | 149 (9.8)
Severe | 5 (0.2) |  | 2 (0.1) | 27 (0.9) | 4 (0.3)
Headache
Any | 703 (22.7) |  | 372 (24.3) | 870 (28.4) | 284 (18.7)
Mild | 530 (17.1) |  | 275 (18.0) | 576 (18.8) | 201 (13.2)
Moderate | 170 (5.5) |  | 91 (5.9) | 286 (9.3) | 82 (5.4)
Severe | 3 (0.1) |  | 6 (0.4) | 8 (0.3) | 1 (0.1)
Chills
Any | 174 (5.6) |  | 84 (5.5) | 301 (9.8) | 66 (4.3)
Mild | 138 (4.5) |  | 69 (4.5) | 205 (6.7) | 52 (3.4)
Moderate | 36 (1.2) |  | 15 (1.0) | 94 (3.1) | 13 (0.9)
Severe | 0 |  | 0 | 2 (0.1) | 1 (0.1)
Vomiting [Mild: 1 to 2 times in 24 hours; Moderate: >2 times in 24 hours; Severe: requires intravenous hydration.]
Any | 63 (2.0) |  | 30 (2.0) | 62 (2.0) | 27 (1.8)
Mild | 52 (1.7) |  | 28 (1.8) | 56 (1.8) | 22 (1.4)
Moderate | 11 (0.4) |  | 2 (0.1) | 5 (0.2) | 5 (0.3)
Severe | 0 |  | 0 | 1 (0.0) | 0
Diarrhea [Mild: 2 to 3 loose stools in 24 hours; Moderate: 4 to 5 loose stools in 24 hours; Severe: 6 or more loose stools in 24 hours.]
Any | 198 (6.4) |  | 75 (4.9) | 166 (5.4) | 76 (5.0)
Mild | 184 (5.9) |  | 72 (4.7) | 149 (4.9) | 70 (4.6)
Moderate | 14 (0.5) |  | 3 (0.2) | 15 (0.5) | 6 (0.4)
Severe | 0 |  | 0 | 2 (0.1) | 0
New or worsened muscle pain
Any | 289 (9.3) |  | 126 (8.2) | 368 (12.0) | 104 (6.8)
Mild | 206 (6.7) |  | 96 (6.3) | 245 (8.0) | 68 (4.5)
Moderate | 82 (2.6) |  | 30 (2.0) | 122 (4.0) | 36 (2.4)
Severe | 1 (0.0) |  | 0 | 1 (0.0) | 0
New or worsened joint pain
Any | 106 (3.4) |  | 70 (4.6) | 159 (5.2) | 57 (3.7)
Mild | 71 (2.3) |  | 56 (3.7) | 103 (3.4) | 42 (2.8)
Moderate | 35 (1.1) |  | 14 (0.9) | 56 (1.8) | 15 (1.0)
Severe | 0 |  | 0 | 0 | 0
Use of antipyretic or pain medication [Severity was not collected for use of antipyretic or pain medication.] | 436 (14.1) |  | 135 (8.8) | 601 (19.6) | 111 (7.3)
Note: Events and use of antipyretic or pain medication were collected in an electronic diary (e-diary) from Day 1 to Day 7 after each dose.

Unsolicited Adverse Events

In the following analyses of Study 3 in participants 5 through 11 years of age, 3,109 participants received COMIRNATY and 1,538 participants received placebo. Among those who received 2 doses of COMIRNATY or placebo, 1,185 participants in the COMIRNATY group and 575 participants in the placebo group had follow-up time ≥4 to <6 months and 296 participants in the COMIRNATY group and 150 participants in the placebo group had follow-up time of >6 months in the blinded placebo-controlled follow-up period.

Among participants who received at least 1 dose of study vaccine, unsolicited adverse events were reported by 333 (10.7%) participants in the COMIRNATY group and 150 (9.8%) participants in the placebo group.

In an analysis of all unsolicited adverse events reported following administration of Dose 1 to one month after administration of Dose 2, the adverse reactions (excluding reactions reported as solicited adverse reactions) in participants who received COMIRNATY compared with participants who received placebo were lymphadenopathy (n=23; 0.7% vs. n=4; 0.3%), nausea (n=7; 0.2% vs. n=3; 0.2%), decreased appetite (n=3; 0.1% vs. n=2; 0.1%), malaise (n=2; 0.1% vs. n=0), and night sweats (n=1; 0.0% vs. n=0).

Serious Adverse Events

Serious adverse events, from administration of Dose 1 to the participant unblinding date, were reported in 8 (0.3%) COMIRNATY recipients and in 2 (0.1%) placebo recipients. No serious adverse events were considered related to vaccination.

Single Dose (Original Monovalent) in Vaccine-Experienced Children 5 Years Through 11 Years of Age

In Phase 2/3 of Study 3, 2,408 participants 5 years through 11 years of age received a first booster dose of COMIRNATY at a median of 7.9 months (range 5.3 to 19.4 months) after completing the primary series. These participants had a median safety follow-up of 6.4 months from vaccination through the data cutoff date of February 28, 2023. The median age was 8.0 years (range 5 through 11 years of age), 50.5% were male and 49.5% were female, 76.3% were White, 5.9% were Black or African American, 16.9% were Hispanic/Latino, 8.2% were Asian, and 0.5% were American Indian/Alaska Native.

Solicited Local and Systemic Adverse Reactions

The frequency of solicited adverse reactions reported in participants receiving a booster dose of COMIRNATY were generally consistent with those reported in pediatric participants receiving COMIRNATY as part of the two-dose series.

Unsolicited Adverse Events

Lymphadenopathy occurred in 46 (1.9%) participants who received a booster dose of COMIRNATY and in 23 (0.7%) participants who received COMIRNATY as a primary series.

Serious Adverse Events

Serious adverse events from study vaccination through 6 months after study vaccination were reported by 10 (0.4%) COMIRNATY recipients. No serious adverse events were considered related to vaccination.

Single Dose (Bivalent Original and BA.4/BA.5) in Vaccine-Experienced Children 5 Years Through 11 Years of Age

In Study 6, 113 participants 5 years through 11 years of age previously vaccinated with a 2-dose primary series and 1 booster dose of COMIRNATY received a second booster (fourth dose) with Pfizer-BioNTech COVID-19 Vaccine, Bivalent (Original and Omicron BA.4/BA.5). Participants received a second booster with Pfizer-BioNTech COVID-19, Bivalent 2.6 to 8.5 months after receiving their third dose with COMIRNATY and had a median follow-up time of 6.3 months (range 1.1 to 6.8 months) up to a data cutoff date of April 20, 2023. The median age of participants was 9 years (range 5 through 11 years of age), 50.4% were male and 49.6% were female, 58.4% were White, 20.4% were Hispanic/Latino, 19.5% were multiracial, 11.5% were Asian, and 8.0% were Black or African American.

Solicited Local and Systemic Adverse Reactions

The frequency of solicited adverse reactions reported in participants receiving a second booster dose of Pfizer-BioNTech COVID-19 Vaccine, Bivalent (Original and BA.4/BA.5) were generally consistent with those reported in pediatric participants receiving COMIRNATY.

Unsolicited Adverse Events

Lymphadenopathy was reported in 1 (0.9%) participant who received Pfizer-BioNTech COVID-19 Vaccine, Bivalent (Original and BA.4/BA.5).

Serious Adverse Events

No serious adverse events were reported.

Single Dose (Monovalent XBB.1.5) in Vaccine-Naïve Children 5 Years Through 11 Years of Age

In a subset of Study 6, the safety of a single dose of COMIRNATY (encoding the viral spike (S) glycoprotein of SARS-CoV-2 Omicron XBB.1.5) was evaluated in 310 COVID-19 vaccine-naïve participants 5 through 11 years of age. Participants had a median follow-up time of 6.4 months (range 1.7 to 6.9 months). The median age of participants was 7.0 years (range 5 through 11 years of age), 47.1% were male and 52.9% were female, 41.3% were White, 52.9% were Black or African American, 52.3% were Hispanic or Latino, 1.9% were Asian, and 0.3% were American Indian/Alaska Native.

Solicited Local and Systemic Adverse Reactions

The frequency of solicited adverse reactions reported in participants who received a single dose of COMIRNATY, monovalent (XBB.1.5) were generally consistent with those previously reported by participants receiving COMIRNATY.

Unsolicited Adverse Events

In an analysis of all unsolicited adverse events through 1 month after study vaccination, unsolicited adverse events were reported by 11 (3.5%) COMIRNATY recipients. The adverse reaction not already captured by solicited local and systemic reactions was decreased appetite (n=1; 0.3%).

Serious Adverse Events

Serious adverse events from study vaccination through 6 months after study vaccination were reported by 3 (1.0%) COMIRNATY recipients. No serious adverse events were considered related to vaccination.

6.2 Postmarketing Experience

The following adverse reactions have been identified during postmarketing use of COMIRNATY, Pfizer-BioNTech COVID-19 Vaccine and Pfizer-BioNTech COVID-19 Vaccine, Bivalent. Because these reactions are reported voluntarily from a population of uncertain size, it is not always possible to reliably estimate their frequency or establish a causal relationship to vaccine exposure.

Cardiac disorders: myocarditis, pericarditis
Gastrointestinal disorders: diarrhea, vomiting
Immune system disorders: severe allergic reactions, including anaphylaxis, and other hypersensitivity reactions (e.g., rash, pruritus, urticaria, angioedema)
Musculoskeletal and connective tissue disorders: pain in extremity (arm)
Nervous system disorders: syncope, dizziness, febrile seizures (in children 5 through 11 years of age)

Cardiovascular Outcomes in Patients Diagnosed With mRNA COVID-19 Vaccine-associated Myocarditis

In a longitudinal retrospective observational cohort study across 38 hospitals in the U.S., information on cardiovascular outcomes was collected on 333 patients 5 through 29 years of age who had been diagnosed with COVID-19 vaccine-associated myocarditis. Among these patients, 322 were confirmed to have received an mRNA COVID-19 vaccine encoding the S glycoprotein of the Original SARS-CoV-2. Of 331 patients, 278 had onset of symptoms following the second dose of a primary series, 33 following the first dose of a primary series, and 20 following a first booster dose^1.

Among 307 patients who had been diagnosed with COVID-19 vaccine-associated myocarditis for whom follow-up information was available, 89 reported cardiac symptoms at a median follow-up of 91 days (interquartile range 25-186 days) post-vaccination^1.

Initial gadolinium-enhanced cardiac magnetic resonance imaging (CMR) was performed on 216 patients, of whom 177 had late gadolinium enhancement (LGE), a marker of myocardial injury. Among 161 patients who had LGE on initial CMR and who had a follow-up gadolinium-enhanced CMR at a median follow-up of 159 days (interquartile range 78-253 days), 98 had persistence of LGE. Overall, the severity of LGE decreased during follow-up. The clinical and prognostic significance of these CMR findings is not known^1.

Limitations of this study include potential selection bias towards patients with more severe myocarditis who are more likely to be hospitalized and have CMR, variability in diagnostic testing, and variability in follow-up^1.

8 USE IN SPECIFIC POPULATIONS

8.1 Pregnancy

Risk Summary

All pregnancies have a risk of birth defect, loss, or other adverse outcomes. In the US general population, the estimated background risk of major birth defects and miscarriage in clinically recognized pregnancies is 2% to 4% and 15% to 20%, respectively. Available data on COMIRNATY administered to pregnant women are insufficient to inform vaccine-associated risks in pregnancy.

A developmental toxicity study has been performed in female rats administered the equivalent of a single human dose of COMIRNATY [encoding the viral spike (S) glycoprotein of SARS-CoV-2 Wuhan-Hu-1 strain (Original)] on 4 occasions, twice prior to mating and twice during gestation. These studies revealed no evidence of harm to the fetus due to the vaccine (see Animal Data).

Clinical Considerations

Disease-Associated Maternal and/or Embryo/Fetal Risk

Pregnant individuals infected with SARS-CoV-2 are at increased risk of severe COVID-19 compared with non-pregnant individuals.

Data

Animal Data

In a developmental toxicity study, 0.06 mL of a vaccine formulation containing the same quantity of nucleoside-modified messenger ribonucleic acid (mRNA) (30 mcg of modRNA) and other ingredients included in a single human dose of COMIRNATY [encoding the viral spike (S) glycoprotein of SARS-CoV-2 Wuhan-Hu-1 strain (Original)] was administered to female rats by the intramuscular route on 4 occasions: 21 and 14 days prior to mating, and on gestation days 9 and 20. No vaccine-related adverse effects on female fertility, fetal development, or postnatal development were reported in the study.

8.2 Lactation

Risk Summary

It is not known whether COMIRNATY is excreted in human milk. Data are not available to assess the effects of COMIRNATY on the breastfed infant or on milk production/excretion. The developmental and health benefits of breastfeeding should be considered along with the mother’s clinical need for COMIRNATY and any potential adverse effects on the breastfed child from COMIRNATY or from the underlying maternal condition. For preventive vaccines, the underlying maternal condition is susceptibility to disease prevented by the vaccine.

8.4 Pediatric Use

Safety and effectiveness of COMIRNATY in individuals 5 years through 17 years of age with at least one underlying condition that puts them at high risk for severe outcomes from COVID-19 is based on safety and effectiveness data in this age group and in adults [see Adverse Reactions (6) and Clinical Studies (14)].

The safety and effectiveness of COMIRNATY in individuals younger than 5 years of age have not been established. Evidence from clinical studies in individuals 6 months through 4 years of age strongly suggests that a single dose of COMIRNATY would be ineffective in individuals younger than 6 months of age.

8.5 Geriatric Use

Of the total number of COMIRNATY recipients in Study 2 as of March 13, 2021 (N = 22,026), 20.7% (n = 4,552) were 65 years of age and older and 4.2% (n = 925) were 75 years of age and older [see Clinical Studies (14.1)]. In Study 4, of 5,081 recipients who received COMIRNATY as the first booster dose, 23.1% (n = 1,175) were 65 years of age and older and 5.2% (n = 265) were 75 years of age and older. In Study 5, of 726 recipients who received Pfizer-BioNTech COVID-19 Vaccine, Bivalent as the second booster dose, 21.9% (n = 159) were 65 years of age and older and 4.8% (n = 35) were 75 years of age and older [see Clinical Studies (14.1)]. No overall differences in safety or effectiveness were observed between these recipients and younger recipients.

8.6 Immunocompromised Individuals

The Centers for Disease Control and Prevention has published considerations related to COVID-19 vaccination for individuals who are moderately to severely immunocompromised (https://www.cdc.gov/vaccines/covid-19/clinical-considerations/covid-19-vaccines-us.html).

11 DESCRIPTION

COMIRNATY (COVID-19 Vaccine, mRNA) is a sterile injectable suspension for intramuscular use.

Single-Dose Prefilled Syringe for Individuals 65 Years of Age and Older and Individuals 12 Years Through 64 Years of Age with at Least One Underlying Condition that Puts Them at High Risk for Severe Outcomes from COVID-19:

Each 0.3 mL dose of COMIRNATY (2025-2026 Formula) is formulated to contain 30 mcg of a nucleoside-modified messenger RNA (modRNA) encoding the viral spike (S) glycoprotein of SARS-CoV-2 Omicron variant sublineage LP.8.1.

Each 0.3 mL dose of COMIRNATY also includes the following ingredients: lipids (0.43 mg ((4-hydroxybutyl)azanediyl)bis(hexane-6,1-diyl)bis(2-hexyldecanoate), 0.05 mg 2-(polyethylene glycol 2000)-N,N-ditetradecylacetamide, 0.09 mg 1,2-distearoyl-sn-glycero-3-phosphocholine, and 0.19 mg cholesterol), 0.06 mg tromethamine, 0.4 mg tromethamine hydrochloride, and 31 mg sucrose.

Single-Dose Vial for Individuals 5 Years Through 11 Years of Age with at Least One Underlying Condition that Puts Them at High Risk for Severe Outcomes from COVID-19:

Each 0.3 mL dose of COMIRNATY (2025-2026 Formula) is formulated to contain 10 mcg of a modRNA encoding the viral spike (S) glycoprotein of SARS-CoV-2 Omicron variant sublineage LP.8.1.

Each 0.3 mL dose of COMIRNATY also includes the following ingredients: lipids (0.14 mg ((4-hydroxybutyl)azanediyl)bis(hexane-6,1-diyl)bis(2-hexyldecanoate), 0.02 mg 2-(polyethylene glycol 2000)-N,N-ditetradecylacetamide, 0.03 mg 1,2-distearoyl-sn-glycero-3-phosphocholine, and 0.06 mg cholesterol), 0.06 mg tromethamine, 0.4 mg tromethamine hydrochloride, and 31 mg sucrose.

COMIRNATY does not contain preservatives.

The vial stoppers are not made with natural rubber latex.

The prefilled syringe tip cap and plunger stopper are not made with natural rubber latex.

12 CLINICAL PHARMACOLOGY

12.1 Mechanism of Action

The nucleoside-modified mRNA in COMIRNATY is formulated in lipid particles, which enable delivery of the mRNA into host cells to allow expression of the SARS-CoV-2 S antigen. The vaccine elicits an immune response to the S antigen, which protects against COVID-19.

13 NONCLINICAL TOXICOLOGY

13.1 Carcinogenesis, Mutagenesis, Impairment of Fertility

COMIRNATY has not been evaluated for the potential to cause carcinogenicity, genotoxicity, or impairment of male fertility. In a developmental toxicity study in rats with COMIRNATY [encoding the viral spike (S) glycoprotein of SARS-CoV-2 Wuhan-Hu-1 strain (Original)] there were no vaccine-related effects on female fertility [see Use in Specific Populations (8.1)].

14 CLINICAL STUDIES

14.1 Adults and Adolescents 12 Years of Age and Older

Efficacy of Two-Dose Series (Original Monovalent) in Vaccine-Naïve Individuals 16 Years of Age and Older

Study 2 is an ongoing, multicenter, multinational, randomized, placebo-controlled, observer-blind, dose-finding, vaccine candidate–selection, and efficacy study in participants 12 years of age and older. Randomization was stratified by age: 12 through 15 years of age, 16 through 55 years of age, or 56 years of age and older, with a minimum of 40% of participants in the ≥56-year stratum. The study excluded participants who were immunocompromised and those who had previous clinical or microbiological diagnosis of COVID-19. Participants with preexisting stable disease, defined as disease not requiring significant change in therapy or hospitalization for worsening disease during the 6 weeks before enrollment, were included as were participants with known stable infection with HIV, hepatitis C virus (HCV), or hepatitis B virus (HBV).

In Study 2, based on data accrued through March 13, 2021, approximately 44,000 participants 12 years of age and older were randomized equally and received 2 doses of COMIRNATY or placebo. Participants are planned to be followed for up to 24 months, for assessments of safety and efficacy against COVID-19.

Overall, among the total participants who received COMIRNATY or placebo, 51.4% and 50.3% were male and 48.6% and 49.7% were female, 79.1% and 79.2% were 16 through 64 years of age, 20.9% and 20.8% were 65 years of age and older, 81.9% and 82.1% were White, 9.5% and 9.6% were Black or African American, 1.0% and 0.9% were American Indian or Alaska Native, 4.4% and 4.3% were Asian, 0.3% and 0.2% Native Hawaiian or other Pacific Islander, 25.6% and 25.4% were Hispanic/Latino, 73.9% and 74.1% were non-Hispanic/Latino, 0.5% and 0.5% did not report ethnicity, 46.0% and 45.7% had comorbidities [participants who have 1 or more comorbidities that increase the risk of severe COVID-19 disease: defined as subjects who had at least 1 of the Charlson comorbidity index category or body mass index (BMI) ≥30 kg/m^2], respectively. The mean age at vaccination was 49.8 and 49.7 years and median age was 51.0 and 51.0 in participants who received COMIRNATY or placebo, respectively.

Efficacy Against COVID-19

The population for the analysis of the protocol pre-specified primary efficacy endpoint included 36,621 participants 12 years of age and older (18,242 in the COMIRNATY group and 18,379 in the placebo group) who did not have evidence of prior infection with SARS-CoV-2 through 7 days after the second dose. The population in the protocol pre-specified primary efficacy analysis included all participants 12 years of age and older who had been enrolled from July 27, 2020, and followed for the development of COVID-19 through November 14, 2020. Participants 18 through 55 years of age and 56 years of age and older began enrollment from July 27, 2020, 16 through 17 years of age began enrollment from September 16, 2020, and 12 through 15 years of age began enrollment from October 15, 2020.

For participants without evidence of SARS-CoV-2 infection prior to 7 days after Dose 2, vaccine efficacy against confirmed COVID-19 occurring at least 7 days after Dose 2 was 95.0% (95% credible interval: 90.3, 97.6), which met the pre-specified success criterion. The case split was 8 COVID-19 cases in the COMIRNATY group compared to 162 COVID-19 cases in the placebo group.

The population for the updated vaccine efficacy analysis included participants 16 years of age and older who had been enrolled from July 27, 2020, and followed for the development of COVID-19 during blinded placebo-controlled follow-up through March 13, 2021, representing up to 6 months of follow-up after Dose 2. There were 12,796 (60.8%) participants in the COMIRNATY group and 12,449 (58.7%) in the placebo group followed for ≥4 months after Dose 2 in the blinded placebo-controlled follow-up period.

SARS-CoV-2 variants of concern identified from COVID-19 cases for this age group from this data cutoff include B.1.1.7 (Alpha) and B.1.351 (Beta). Representation of identified variants among cases in vaccine versus placebo recipients did not suggest decreased vaccine effectiveness against these variants.

The updated vaccine efficacy information is presented in Table 13.

Table 13: Vaccine Efficacy – First COVID-19 Occurrence From 7 Days After Dose 2, by Age Subgroup – Participants 16 Years of Age and Older Without Evidence of Infection and Participants With or Without Evidence of Infection Prior to 7 Days After Dose 2 – Evaluable Efficacy (7 Days) Population During the Placebo-Controlled Follow-up Period
First COVID-19 occurrence from 7 days after Dose 2 in participants without evidence of prior SARS-CoV-2 infection [Participants who had no evidence of past SARS-CoV-2 infection (i.e., N-binding antibody [serum] negative at Visit 1 and SARS-CoV-2 not detected by NAAT [nasal swab] at Visits 1 and 2) and had negative NAAT (nasal swab) at any unscheduled visit prior to 7 days after Dose 2 were included in the analysis.]
Subgroup | COMIRNATY [Vaccine encoding the viral spike (S) glycoprotein of SARS-CoV-2 Wuhan-Hu-1 strain (Original).] N [N = Number of participants in the specified group.] =19,993 Cases n1 [n1 = Number of participants meeting the endpoint definition.] Surveillance Time [Total surveillance time in 1,000 person-years for the given endpoint across all participants within each group at risk for the endpoint. Time period for COVID-19 case accrual is from 7 days after Dose 2 to the end of the surveillance period.] (n2 [n2 = Number of participants at risk for the endpoint.]) | Placebo N=20,118 Cases n1 Surveillance Time (n2) | Vaccine Efficacy % (95% CI [Two-sided confidence interval (CI) for vaccine efficacy is derived based on the Clopper and Pearson method adjusted to the surveillance time.])
All participants | 77 6.092 (19,711) | 833 5.857 (19,741) | 91.1 (88.8, 93.1)
16 through 64 years | 70 4.859 (15,519) | 709 4.654 (15,515) | 90.5 (87.9, 92.7)
65 years and older | 7 1.233 (4192) | 124 1.202 (4226) | 94.5 (88.3, 97.8)
First COVID-19 occurrence from 7 days after Dose 2 in participants with or without evidence of prior SARS-CoV-2 infection
Subgroup | COMIRNATY N=21,047 Cases n1 Surveillance Time (n2) | Placebo N=21,210 Cases n1 Surveillance Time (n2) | Vaccine Efficacy % (95% CI)
All participants | 81 6.340 (20,533) | 854 6.110 (20,595) | 90.9 (88.5, 92.8)
16 through 64 years | 74 5.073 (16,218) | 726 4.879 (16,269) | 90.2 (87.5, 92.4)
65 years and older | 7 1.267 (4315) | 128 1.232 (4326) | 94.7 (88.7, 97.9)
Abbreviations: CI = confidence interval; NAAT = nucleic acid amplification test; SARS-CoV-2 = severe acute respiratory syndrome coronavirus 2.
Note: Confirmed cases were determined by Reverse Transcription-Polymerase Chain Reaction (RT-PCR) and at least 1 symptom consistent with COVID-19 (symptoms included: fever; new or increased cough; new or increased shortness of breath; chills; new or increased muscle pain; new loss of taste or smell; sore throat; diarrhea; vomiting).

Subgroup analyses of vaccine efficacy (although limited by small numbers of cases in some subgroups) did not suggest meaningful differences in efficacy across sex, ethnic groups, geographies, or for participants with obesity or medical comorbidities associated with high risk of severe COVID-19.

Efficacy Against Severe COVID-19

Efficacy analyses of secondary efficacy endpoints supported the benefit of COMIRNATY in preventing severe COVID-19. Vaccine efficacy against severe COVID-19 is presented only for participants with or without prior SARS-CoV-2 infection (Table 14) as the COVID-19 case counts in participants without prior SARS-CoV-2 infection were the same as those in participants with or without prior SARS-CoV-2 infection in both the COMIRNATY and placebo groups.

Table 14: Vaccine Efficacy – First Severe COVID-19 Occurrence in Participants 16 Years of Age and Older With or Without [Participants who had no evidence of past SARS-CoV-2 infection (i.e., N-binding antibody [serum] negative at Visit 1 and SARS-CoV-2 not detected by NAAT [nasal swab] at Visits 1 and 2) and had negative NAAT (nasal swab) at any unscheduled visit prior to 7 days after Dose 2 were included in the analysis.] Prior SARS-CoV-2 Infection Based on Protocol [Severe illness from COVID-19 is defined in the protocol as confirmed COVID-19 and presence of at least 1 of the following: • Clinical signs at rest indicative of severe systemic illness (respiratory rate ≥30 breaths per minute, heart rate ≥125 beats per minute, saturation of oxygen ≤93% on room air at sea level, or ratio of arterial oxygen partial pressure to fractional inspired oxygen <300 mm Hg); • Respiratory failure [defined as needing high flow oxygen, noninvasive ventilation, mechanical ventilation, or extracorporeal membrane oxygenation (ECMO)]; • Evidence of shock (systolic blood pressure <90 mm Hg, diastolic blood pressure <60 mm Hg, or requiring vasopressors); • Significant acute renal, hepatic, or neurologic dysfunction; • Admission to an Intensive Care Unit; • Death.] or Centers for Disease Control and Prevention (CDC) [Severe illness from COVID-19 as defined by CDC is confirmed COVID-19 and presence of at least 1 of the following: • Hospitalization; • Admission to the Intensive Care Unit; • Intubation or mechanical ventilation; • Death.] Definition From 7 Days After Dose 2 – Evaluable Efficacy (7 Days) Population During the Placebo-Controlled Follow-up
Vaccine Efficacy – First Severe COVID-19 Occurrence
 | COMIRNATY [Vaccine encoding the viral spike (S) glycoprotein of SARS-CoV-2 Wuhan-Hu-1 strain (Original).] Cases n1 [n1 = Number of participants meeting the endpoint definition.] Surveillance Time [Total surveillance time in 1,000 person-years for the given endpoint across all participants within each group at risk for the endpoint. Time period for COVID-19 case accrual is from 7 days after Dose 2 to the end of the surveillance period.] (n2 [n2 = Number of participants at risk for the endpoint.]) | Placebo Cases n1 Surveillance Time (n2) | Vaccine Efficacy % (95% CI [Two-side confidence interval (CI) for vaccine efficacy is derived based on the Clopper and Pearson method adjusted to the surveillance time.])
7 days after Dose 2 | 1 6.353 (20,540) | 21 6.237 (20,629) | 95.3 (70.9, 99.9)
Vaccine Efficacy – First Severe COVID-19 Occurrence Based on CDC Definition
 | COMIRNATY Cases n1 Surveillance Time (n2) | Placebo Cases n1 Surveillance Time (n2) | Vaccine Efficacy % (95% CI)
7 days after Dose 2 | 0 6.345 (20,513) | 31 6.225 (20,593) | 100 (87.6, 100.0)
Abbreviations: CI = confidence interval; NAAT = nucleic acid amplification test; SARS-CoV-2 = severe acute respiratory syndrome coronavirus 2.
Note: Confirmed cases were determined by Reverse Transcription-Polymerase Chain Reaction (RT-PCR) and at least 1 symptom consistent with COVID-19 (symptoms included: fever; new or increased cough; new or increased shortness of breath; chills; new or increased muscle pain; new loss of taste or smell; sore throat; diarrhea; vomiting).

Efficacy and Immunogenicity of Two-Dose Series (Original Monovalent) in Vaccine-Naïve Adolescents 12 Through 15 Years of Age

A descriptive efficacy analysis of Study 2 has been performed in 2,260 adolescents 12 through 15 years of age evaluating confirmed COVID-19 cases accrued up to a data cutoff date of September 2, 2021.

The vaccine efficacy information in adolescents 12 through 15 years of age is presented in Table 15.

Table 15: Vaccine Efficacy – First COVID-19 Occurrence From 7 Days After Dose 2: Without Evidence of Infection and With or Without Evidence of Infection Prior to 7 Days After Dose 2 – Blinded Placebo-Controlled Follow-up Period, Adolescents 12 Through 15 Years of Age Evaluable Efficacy (7 Days) Population
First COVID-19 occurrence from 7 days after Dose 2 in adolescents 12 through 15 years of age without evidence of prior SARS-CoV-2 infection [Participants who had no evidence of past SARS-CoV-2 infection (i.e., N-binding antibody [serum] negative at Visit 1 and SARS-CoV-2 not detected by NAAT [nasal swab] at Visits 1 and 2) and had negative NAAT (nasal swab) at any unscheduled visit prior to 7 days after Dose 2 were included in the analysis.]
 | COMIRNATY [Vaccine encoding the viral spike (S) glycoprotein of SARS-CoV-2 Wuhan-Hu-1 strain (Original).] N [N = Number of participants in the specified group.] =1057 Cases n1 [n1 = Number of participants meeting the endpoint definition.] Surveillance Time [Total surveillance time in 1,000 person-years for the given endpoint across all participants within each group at risk for the endpoint. Time period for COVID-19 case accrual is from 7 days after Dose 2 to the end of the surveillance period.] (n2 [n2 = Number of participants at risk for the endpoint.]) | Placebo N=1030 Cases n1 Surveillance Time (n2) | Vaccine Efficacy % (95% CI [Two-side confidence interval (CI) for vaccine efficacy is derived based on the Clopper and Pearson method adjusted for surveillance time.])
Adolescents 12 through 15 years of age | 0 0.343 (1043) | 28 0.322 (1019) | 100.0 (86.8, 100.0)
First COVID-19 occurrence from 7 days after Dose 2 in adolescents 12 through 15 years of age with or without evidence of prior SARS-CoV-2 infection
 | COMIRNATY N=1119 Cases n1 Surveillance Time (n2) | Placebo N=1109 Cases n1 Surveillance Time (n2) | Vaccine Efficacy % (95% CI)
Adolescents 12 through 15 years of age | 0 0.362 (1098) | 30 [The only SARS-CoV-2 variant of concern identified from COVID-19 cases in this age group from this data cutoff was B.1.1.7 (Alpha).] 0.345 (1088) | 100.0 (87.5, 100.0)
Abbreviations: CI = confidence interval; NAAT = nucleic acid amplification test; SARS-CoV-2 = severe acute respiratory syndrome coronavirus 2.
Note: Confirmed cases were determined by Reverse Transcription-Polymerase Chain Reaction (RT-PCR) and at least 1 symptom consistent with COVID-19 (symptoms included: fever; new or increased cough; new or increased shortness of breath; chills; new or increased muscle pain; new loss of taste or smell; sore throat; diarrhea; vomiting).

In Study 2, an analysis of SARS-CoV-2 50% neutralizing titers (NT50) 1 month after Dose 2 in a randomly selected subset of participants demonstrated noninferior immune responses (within 1.5-fold) comparing adolescents 12 through 15 years of age to participants 16 through 25 years of age who had no serological or virological evidence of past SARS-CoV-2 infection up to 1 month after Dose 2 (Table 16).

Table 16: Summary of Geometric Mean Ratio for 50% Neutralizing Titer – Comparison of Adolescents 12 Through 15 Years of Age to Participants 16 Through 25 Years of Age (Immunogenicity Subset) – Participants Without Evidence of Infection up to 1 Month After Dose 2 – Dose 2 Evaluable Immunogenicity Population
 |  | COMIRNATY [Vaccine encoding the viral spike (S) glycoprotein of SARS-CoV-2 Wuhan-Hu-1 strain (Original).]
 |  | 12 Through 15 Years n [n = Number of participants with valid and determinate assay results for the specified assay at the given dose/sampling time point.] =190 | 16 Through 25 Years n=170 | 12 Through 15 Years/ 16 Through 25 Years
Assay | Time Point [Protocol-specified timing for blood sample collection.] | GMT [GMTs and 2-sided 95% CIs were calculated by exponentiating the mean logarithm of the titers and the corresponding CIs (based on the Student t distribution). Assay results below the LLOQ were set to 0.5 × LLOQ.] (95% CI) | GMT (95% CI) | GMR [GMRs and 2-sided 95% CIs were calculated by exponentiating the mean difference of the logarithms of the titers (Group 1 [12 through 15 years of age] – Group 2 [16 through 25 years of age]) and the corresponding CI (based on the Student t distribution).] (95% CI) | Met Noninferiority Objective [Noninferiority is declared if the lower bound of the 2-sided 95% CI for the GMR is greater than 0.67.] (Y/N)
SARS-CoV-2 neutralization assay - NT50 (titer) [SARS-CoV-2 NT50 were determined using the SARS-CoV-2 mNeonGreen Virus Microneutralization Assay. The assay uses a fluorescent reporter virus derived from the USA_WA1/2020 strain and virus neutralization is read on Vero cell monolayers. The sample NT50 is defined as the reciprocal serum dilution at which 50% of the virus is neutralized.] | 1 month after Dose 2 | 1253.6 (1117.7, 1406.1) | 708.1 (625.9, 801.1) | 1.77 (1.50, 2.09) | Y
Abbreviations: CI = confidence interval; GMR = geometric mean ratio; GMT = geometric mean titer; LLOQ = lower limit of quantitation; NAAT = nucleic acid amplification test; NT50 = 50% neutralizing titer; SARS-CoV-2 = severe acute respiratory syndrome coronavirus 2.
Note: Participants who had no serological or virological evidence (up to 1 month after receipt of the last dose) of past SARS-CoV-2 infection (i.e., N-binding antibody [serum] negative at Visit 1 and SARS-CoV-2 not detected by NAAT [nasal swab] at Visits 1 and 2), and had negative NAAT (nasal swab) at any unscheduled visit up to 1 month after Dose 2 were included in the analysis.

Immunogenicity of Single Dose (Original Monovalent) in Vaccine-Experienced Adults 18 Years Through 55 Years of Age

Effectiveness of a booster dose of COMIRNATY was based on an assessment of 50% neutralizing antibody titers (NT50) against SARS-CoV-2 reference strain (USA_WA1/2020) in Study 2 participants 18 through 55 years of age (n = 200 – 212) who had no serological or virological evidence of past SARS‑CoV‑2 infection up to 1 month after the booster vaccination. Analyses of NT50 1 month after the booster dose compared to 1 month after the primary series demonstrated noninferiority for both geometric mean ratio (GMR) [3.26 (97.5% CI: 2.76, 3.86)] and difference in seroresponse rates (percentage) [4.5% (97.5% CI: 1.0, 7.9)]. Seroresponse for a participant was defined as achieving a ≥4-fold rise in NT50 from baseline (before primary series).

Immunogenicity of a Single Dose (Bivalent Original and BA.4/BA.5) in Vaccine-Experienced Individuals 12 Years of Age and Older

In an analysis of a subset from Study 5, 105 participants 12 through 17 years of age, 297 participants 18 through 55 years of age, and 286 participants 56 years of age and older who had previously received a 2-dose primary series and 1 booster dose with COMIRNATY received a second booster dose of Pfizer-BioNTech COVID-19 Vaccine, Bivalent. In participants 12 through 17 years of age, 18 through 55 years of age, and 56 years of age and older, 75.2%, 71.7% and 61.5% were positive for SARS-CoV-2 at baseline, respectively.

Analyses of NT50 against Omicron BA.4/BA.5 and against reference strain among participants 56 years of age and older who received a second booster dose of Pfizer-BioNTech COVID-19 Vaccine, Bivalent in Study 5 compared to a subset of participants from Study 4 who received a second booster dose of COMIRNATY demonstrated superiority of Pfizer-BioNTech COVID-19 Vaccine, Bivalent to COMIRNATY based on GMR and noninferiority based on difference in seroresponse rates with respect to anti-Omicron BA.4/BA.5 response, and noninferiority of anti-reference strain immune response based on GMR (Table 17 and Table 18).

Analyses of NT50 against Omicron BA.4/BA.5 among participants 18 through 55 years of age compared to participants 56 years of age and older who received a second booster dose of Pfizer-BioNTech COVID-19 Vaccine, Bivalent in Study 5 demonstrated noninferiority of anti-Omicron BA.4/BA.5 response among participants 18 through 55 years of age to participants 56 years of age and older for both GMR and difference in seroresponse rates (Table 17 and Table 18).

The study also assessed the level of NT50 against the anti-Omicron BA.4/BA.5 and original SARS-CoV-2 strains pre-vaccination and 1 month after vaccination in participants who received a second booster dose (Table 19).

Table 17: Geometric Mean Titer Ratios – Study 5 COMIRNATY – Participants With or Without Evidence of Infection – Evaluable Immunogenicity Population
SARS-CoV-2 Neutralization Assay | Sampling Time Point [Protocol-specified timing for blood sample collection.] | Pfizer-BioNTech COVID-19 Vaccine, Bivalent [Vaccine encoding the viral spike (S) glycoprotein of SARS-CoV-2 Wuhan-Hu-1 strain (Original) and Omicron variant lineages BA.4 and BA.5 (Omicron BA.4/BA.5).]; Study 5 |  |  |  | COMIRNATY [Vaccine encoding the viral spike (S) glycoprotein of SARS-CoV-2 Wuhan-Hu-1 strain (Original).]; Subset of Study 4 |  | Age Group Comparison | Vaccine Group Comparison
SARS-CoV-2 Neutralization Assay | Sampling Time Point [Protocol-specified timing for blood sample collection.] | 18 Through 55 Years of Age |  | 56 Years of Age and Older |  | 56 Years of Age and Older |  | Pfizer-BioNTech COVID-19 Vaccine, Bivalent; 18 Through 55 Years of Age/≥56 Years of Age | ≥56 Years of Age; Pfizer-BioNTech COVID-19 Vaccine, Bivalent/ COMIRNATY
SARS-CoV-2 Neutralization Assay | Sampling Time Point [Protocol-specified timing for blood sample collection.] | n [n = Number of participants with valid and determinate assay results for the specified assay at the given sampling time point.] | GMT [GMTs and 2-sided 95% CIs were calculated by exponentiating the mean logarithm of the titers and the corresponding CIs (based on the Student t distribution). Assay results below the LLOQ were set to 0.5 × LLOQ.]; (95% CI) | n | GMT; (95% CI) | n | GMT; (95% CI) | GMR [GMRs and 2-sided 95% CIs were calculated by exponentiating the difference of LS means and corresponding CIs based on analysis of logarithmically transformed neutralizing titers using a linear regression model with terms of baseline neutralizing titer (log scale) and vaccine group or age group.] (95% CI) | GMR (95% CI)
Omicron BA.4/BA.5 - NT50 (titer) [SARS-CoV-2 NT50 were determined using a validated 384-well assay platform (original strain [USA-WA1/2020, isolated in January 2020] and Omicron B.1.1.529 subvariant BA.4/BA.5).] | 1 Month | 297 | 4455.9; (3851.7, 5154.8) | 284 | 4158.1; (3554.8, 4863.8) | 282 | 938.9; (802.3, 1098.8) | 0.98; (0.83, 1.16) [Noninferiority is declared if the lower bound of the 2-sided 95% CI for the GMR is greater than 0.67.] | 2.91; (2.45, 3.44) [Superiority is declared if the lower bound of the 2-sided 95% CI for the GMR is greater than 1.]
Reference Strain –; NT50 (titer) | 1 Month | - | - | 286 | 16250.1; (14499.2, 18212.4) | 289 | 10415.5; (9366.7, 11581.8) | - | 1.38; (1.22, 1.56) [Noninferiority is declared if the lower bound of the 2-sided 95% CI for the GMR is greater than 0.67 and the point estimate of the GMR is ≥0.8.]
Abbreviations: GMT = geometric mean titer; LLOQ = lower limit of quantitation; N-binding = SARS-CoV-2 nucleoprotein–binding; NAAT = nucleic acid amplification test; NT50 = 50% neutralizing titer; SARS-CoV-2 = severe acute respiratory syndrome coronavirus 2.

Table 18: Difference in Percentages of Participants With Seroresponse – Pfizer-BioNTech COVID-19 Vaccine, Bivalent from Study 5 and COMIRNATY from Subset of Study 4 – Participants With or Without Evidence of Infection – Evaluable Immunogenicity Population
 |  | Pfizer-BioNTech COVID-19 Vaccine, Bivalent [Vaccine encoding the viral spike (S) glycoprotein of SARS-CoV-2 Wuhan-Hu-1 strain (Original) and Omicron variant lineages BA.4 and BA.5 (Omicron BA.4/BA.5).]; Study 5 |  |  |  | COMIRNATY [Vaccine encoding the viral spike (S) glycoprotein of SARS-CoV-2 Wuhan-Hu-1 strain (Original).]; Subset of Study 4 |  | Age Group Comparison | Vaccine Group Comparison
 |  | 18 Through 55 Years of Age |  | 56 Years of Age and Older |  | 56 Years of Age and Older |  | Pfizer-BioNTech COVID-19 Vaccine, Bivalent; 18 Through 55 Years of Age/≥56 Years of Age | ≥56 Years of Age; Pfizer-BioNTech COVID-19 Vaccine, Bivalent / COMIRNATY
SARS-CoV-2 Neutralization Assay | Sampling Time Point [Protocol-specified timing for blood sample collection.] | n [N = Number of participants with valid and determinate assay results for the specified assay at both the pre-vaccination time point and the given sampling time point. This value is the denominator for the percentage calculation.] | N [n = Number of participants with seroresponse for the given assay at the given sampling time point.] (%); (95% CI [Exact 2-sided CI, based on the Clopper and Pearson method.]) | n | N (%); (95% CI) | n | N (%); (95% CI) | Difference [Difference in proportions, expressed as a percentage.] (95% CI [2-sided CI based on the Miettinen and Nurminen method stratified by baseline neutralizing titer category (<median, ≥ median) for the difference in proportions. The median of baseline neutralizing titers was calculated based on the pooled data in 2 comparator groups.]) | Difference (95% CI)
Omicron BA.4/BA.5 - NT50 (titer) [SARS-CoV-2 NT50 were determined using a validated 384-well assay platform (Omicron B.1.1.529 subvariant BA.4/BA.5).] | 1 Month | 294 | 180 (61.2); (55.4, 66.8) | 282 | 188 (66.7); (60.8, 72.1) | 273 | 127 (46.5); (40.5, 52.6) | -3.03; (-9.68, 3.63) [Noninferiority is declared if the lower bound of the 2-sided 95% CI for the difference in percentages of participants with seroresponse is >-10%.] | 26.77; (19.59, 33.95) [Noninferiority is declared if the lower bound of the 2-sided 95% CI for the difference in percentages of participants with seroresponse is >-5%.]
Abbreviations: LLOQ = lower limit of quantitation; NT50 = 50% neutralizing titer; SARS-CoV-2 = severe acute respiratory syndrome coronavirus 2.
Note: Seroresponse is defined as achieving a ≥4-fold rise from baseline. If the baseline measurement is below the LLOQ, a post-vaccination assay result ≥4 × LLOQ is considered a seroresponse.

Table 19: Geometric Mean Titers – Pfizer-BioNTech COVID-19 Vaccine, Bivalent Groups Subset of Study 5 – Prior to and 1 Month After Second Booster – Participants 12 Years of Age and Older – Evaluable Immunogenicity Population
SARS-CoV-2 Neutralization Assay | Sampling Time Point [Protocol-specified timing for blood sample collection.] | Pfizer-BioNTech COVID-19 Vaccine, Bivalent [Vaccine encoding the viral spike (S) glycoprotein of SARS-CoV-2 Wuhan-Hu-1 strain (Original) and Omicron variant lineages BA.4 and BA.5 (Omicron BA.4/BA.5).]
SARS-CoV-2 Neutralization Assay | Sampling Time Point [Protocol-specified timing for blood sample collection.] | 12 Through 17 Years of Age |  | 18 Through 55 Years of Age |  | 56 Years of Age and Older
SARS-CoV-2 Neutralization Assay | Sampling Time Point [Protocol-specified timing for blood sample collection.] | n [n = Number of participants with valid and determinate assay results for the specified assay at the given sampling time point.] | GMT [GMTs and 2-sided 95% CIs were calculated by exponentiating the mean logarithm of the titers and the corresponding CIs (based on the Student t distribution). Assay results below the LLOQ were set to 0.5 × LLOQ.]; (95% CI) | n | GMT; (95% CI) | n | GMT; (95% CI)
Omicron BA.4/BA.5 - NT50 (titer) [SARS-CoV-2 NT50 were determined using a validated 384-well assay platform (original strain [USA-WA1/2020, isolated in January 2020] and Omicron B.1.1.529 subvariant BA.4/BA.5).] | Pre-; vaccination | 104 | 1105.8; (835.1, 1464.3) | 294 | 569.6; (471.4, 688.2) | 284 | 458.2; (365.2, 574.8)
Omicron BA.4/BA.5 - NT50 (titer) [SARS-CoV-2 NT50 were determined using a validated 384-well assay platform (original strain [USA-WA1/2020, isolated in January 2020] and Omicron B.1.1.529 subvariant BA.4/BA.5).] | 1 Month | 105 | 8212.8; (6807.3, 9908.7) | 297 | 4455.9; (3851.7, 5154.8) | 284 | 4158.1; (3554.8, 4863.8)
Reference strain - NT50 (titer) | Pre-vaccination | 105 | 6863.3; (5587.8, 8430.1) | 296 | 4017.3; (3430.7, 4704.1) | 284 | 3690.6; (3082.2, 4419.0)
Reference strain - NT50 (titer) | 1 Month | 105 | 23641.3; (20473.1, 27299.8) | 296 | 16323.3; (14686.5, 18142.6) | 286 | 16250.1; (14499.2, 18212.4)
Abbreviations: GMT = geometric mean titer; LLOQ = lower limit of quantitation; N-binding = SARS-CoV-2 nucleoprotein–binding; NAAT = nucleic acid amplification test; NT50 = 50% neutralizing titer; SARS-CoV-2 = severe acute respiratory syndrome coronavirus 2.

Immunogenicity of a Single Dose (Bivalent Alpha and Delta) in Seropositive, Vaccine-Naïve Adults 18 Years of Age and Older

In a post-hoc analysis in a subset of participants 18 through 85 years of age enrolled in Study 7 (NCT05004181), immunogenicity of a single dose of a Pfizer-BioNTech bivalent COVID-19 vaccine containing equal quantities of modRNA (30 mcg total) encoding the viral spike (S) glycoprotein for the Alpha and Delta SARS-CoV-2 variants [not authorized or approved in the U.S., hereafter referred to as bivalent vaccine (Alpha and Delta)] was assessed in COVID-19 vaccine-naïve participants with evidence of prior SARS-CoV-2 infection (n = 262) compared to participants without prior SARS-CoV-2 infection who received 2 doses of COMIRNATY in Study 2 (n = 275). Among Study 7 participants, 253 were from study sites in South Africa and 9 were from study sites in the U.S. The immunogenicity of the bivalent Alpha and Delta vaccine is relevant to COMIRNATY because these vaccines are manufactured using the same process with differences only in the encoded spike proteins.

Table 20 presents demographic characteristics for participants in the immunogenicity analysis set.

Table 20: Demographic Characteristics – Subset of Participants from Study 7 and Study 2 – Reference Strain Neutralization – Immunogenicity Analysis Set
 | Study 7; Single Dose of Bivalent Vaccine (Alpha and Delta); With Evidence of Prior Infection; (N [N = Number of participants in the specified group. This value is the denominator for the percentage calculations.] =262); N [n = Number of participants with the specified characteristic.] (%) | Study 2; Two Doses of COMIRNATY [Vaccine encoding the viral spike (S) glycoprotein of SARS-CoV-2 Wuhan-Hu-1 strain (Original).]; Without Evidence of Infection; (N=275); N (%)
Sex
Male | 109 (41.6) | 113 (41.1)
Female | 153 (58.4) | 162 (58.9)
Age at Vaccination (Years)
Mean (SD) | 42.9 (16.21) | 42.7 (16.08)
Median | 41.0 | 40.0
Min, max | (18,84) | (18, 84)
Race
White | 4 (1.5) | 230 (83.6)
Black or African American | 169 (64.5) | 25 (9.1)
American Indian or Alaska Native | 0 | 2 (0.7)
Asian | 0 | 7 (2.5)
Other [Includes multiracial and not reported.] | 89 (34.0) | 11 (4.0)
Ethnicity
Hispanic or Latino | 5 (1.9) | 83 (30.2)
Not Hispanic or Latino | 255 (97.3) | 192 (69.8)
Not reported | 2 (0.8) | 0

The objective of this analysis was to assess noninferiority with respect to level of 50% neutralizing titer (NT50) and to the seroresponse rate to the reference strain induced by a single dose of the bivalent Alpha and Delta vaccine in COVID-19 vaccine-naïve participants with evidence of prior infection relative to participants without evidence of SARS-CoV-2 infection who received 2 doses of COMIRNATY.

Noninferiority of the reference strain immune response with respect to level of NT50 was met, as the lower bound of the 2-sided 95% CI for the geometric mean ratio (GMR) was >0.67 (Table 21). Noninferiority of the seroresponse rate to the reference strain was not met, as the lower bound of the 2-sided 95% CIs for the difference in seroresponse rate of reference strain was -10.04%, below the noninferiority margin of -10% (Table 22).

Table 21: Geometric Mean Ratios – Single Dose of Bivalent Vaccine (Alpha and Delta) in Vaccine-Naïve Participants from Study 7 With Evidence of Prior SARS-CoV-2 Infection Compared to 2 Doses of COMIRNATY in a Subset of Participants from Study 2 Without Evidence of SARS-CoV-2 Infection – Reference Strain Neutralization – Immunogenicity Analysis Set
 | Study 7; Single Dose of Bivalent Vaccine (Alpha and Delta); With Evidence of Prior Infection [Participants with positive N-binding antibody result at baseline, positive NAAT result prior to vaccination, or medical history or adverse event of COVID-19 prior to vaccination.]; 3 Weeks After Dose 1 [Protocol-specified timing for blood sample collection.] |  | Study 2; Two Doses of COMIRNATY [Vaccine encoding the viral spike (S) glycoprotein of SARS-CoV-2 Wuhan-Hu-1 strain (Original).]; Without Evidence of Infection [Participants who had no serological or virological evidence (up to the 1-month post–Dose 2 blood sample collection) of past SARS-CoV-2 infection (i.e., negative N-binding antibody [serum] result at the Dose 1 and 1-month post–Dose 2 visits, negative NAAT [nasal swab] at the Dose 1 and Dose 2 visits, and any unscheduled visit [up to the 1-month post–Dose 2 blood sample collection]) and had no medical history of COVID-19 were included in the analysis.]; 1 Month After Dose 2 |  | Bivalent Vaccine (Alpha and Delta) With Evidence of Prior Infection/; COMIRNATY Without Evidence of Infection
SARS-CoV-2 Neutralization Assay | n [n = Number of participants with valid and determinate assay results for the specified assay at the given sampling time point.] | GMT [GMTs and 2-sided 95% CIs were calculated by exponentiating the mean logarithm of the titers and the corresponding CIs (based on the Student t distribution). Assay results below the LLOQ were set to 0.5 × LLOQ.]; (95% CI) | n | GMT; (95% CI) | GMR [GMRs and 2-sided 95% CIs were calculated by exponentiating the difference of LS means and corresponding CIs based on the analysis of logarithmically transformed neutralizing titers using a linear regression model with terms of age, sex, and group. Assay results below the LLOQ were set to 0.5 × LLOQ.]; (95% CI)
Reference strain - NT50 (titer) [SARS-CoV-2 NT50 were determined using a validated 384-well assay platform (original strain [USA-WA1/2020, isolated in January 2020]).] | 262 | 17404.2; (15485.1, 19561.1) | 275 | 1328.1; (1183.1, 1491.0) | 13.12; (11.14, 15.45) [Noninferiority is declared if the lower bound of the 2-sided 95% CI for the GMR is greater than 0.67.]
Abbreviations: CI = confidence interval; GMR = geometric mean ratio; GMT = geometric mean titer; LLOQ = lower limit of quantitation; N-binding = SARS-CoV-2 nucleoprotein–binding; NAAT = nucleic acid amplification test; NT50 = 50% neutralizing titer; SARS-CoV-2 = severe acute respiratory syndrome coronavirus 2.

Table 22: Difference in Percentages of Participants With Seroresponse – Bivalent Vaccine (Alpha and Delta) in Vaccine-Naïve Participants from Study 7 With Evidence of Prior SARS-CoV-2 Infection Compared to 2 Doses of COMIRNATY in a Subset of Participants from Study 2 Without Evidence of Prior SARS-CoV-2 Infection – Reference Strain Neutralization – Immunogenicity Analysis Set
 | Study 7; Bivalent Vaccine (Alpha and Delta) With Evidence of Prior Infection [Participants with positive N-binding antibody result at baseline, positive NAAT result prior to vaccination, or medical history or adverse event of COVID-19 prior to vaccination.]; 3 Weeks After Dose 1 [Protocol-specified timing for blood sample collection.] |  | Study 2; COMIRNATY [Vaccine encoding the viral spike (S) glycoprotein of SARS-CoV-2 Wuhan-Hu-1 strain (Original).]; Without Evidence of Prior Infection [Participants who had no serological or virological evidence (up to the 1-month post–Dose 2 blood sample collection) of past SARS-CoV-2 infection (i.e., negative N-binding antibody [serum] result at the Dose 1 and 1-month post–Dose 2 visits, negative NAAT [nasal swab] at the Dose 1 and Dose 2 visits, and any unscheduled visit [up to the 1-month post–Dose 2 blood sample collection]) and had no medical history of COVID-19 were included in the analysis.]; 1 Month After Dose 2 |  | Bivalent Vaccine (Alpha and Delta); With Evidence of Prior Infection; Minus; COMIRNATY; Without Evidence of Prior Infection
SARS-CoV-2 Neutralization Assay | N [N = Number of participants with valid and determinate assay results for the specified assay at both the pre-vaccination time point and the given sampling time point. This value is the denominator for the percentage calculation.] | n [n = Number of participants with seroresponse for the given assay at the given sampling time point.] (%); (95% CI [Exact 2-sided CI, based on the Clopper and Pearson method.]) | N | n (%); (95% CI) | Difference % [Adjusted difference in proportions estimated using minimum risk weights and stratified by sex and age group (18 to 55 years, 56 to 85 years), expressed as a percentage.] | 95% CI [2-sided CI based on the Newcombe method stratified by sex and age group (18 to 55 years, 56 to 85 years) with minimum risk weights for the difference in proportions.]
Reference strain – NT50 (titer) [SARS-CoV-2 NT50 were determined using a validated 384-well assay platform (original strain [USA-WA1/2020, isolated in January 2020]).] | 260 | 223 (85.8); (80.9, 89.8) | 275 | 249 (90.5); (86.5, 93.7) | -4.55 | (-10.04, 0.83) [Noninferiority is declared if the lower bound of the 2-sided 95% CI for the difference in percentages of participants with seroresponse is >-10%.]
Abbreviations: CI = confidence interval; N-binding = SARS-CoV-2 nucleoprotein–binding; NAAT = nucleic acid amplification test; NT50 = 50% neutralizing titer; SARS-CoV-2 = severe acute respiratory syndrome coronavirus 2.

Concomitant Administration of COMIRNATY (Original Monovalent) With Influenza Vaccine in Adults 18 Years Through 64 Years of Age

In Study 8, a Phase 3 multicenter, randomized, observer-blind study, 1,134 participants 18 through 64 years of age who had received 3 doses of COMIRNATY at least 3 months prior were randomized in a 1:1 ratio to receive either COMIRNATY concomitantly administered with Influenza Vaccine (Afluria Quadrivalent) followed 1 month later by placebo (Group 1, n = 568) or influenza vaccine with placebo followed 1 month later with COMIRNATY (Group 2, n = 566).

Full-length spike (S)-binding IgG responses to COMIRNATY and influenza strain-specific hemagglutination inhibition (HAI) titers were assessed 1-month post-vaccination in each group.

The noninferiority criteria (lower bound of the 2-sided 95% CI >0.67) for the comparison of concomitant administration versus separate administration were met. The GMC ratio of full-length S-binding IgG levels of SARS-CoV-2 Wuhan-Hu-1 strain (Original) (Group 1/Group 2) was 0.83 [95% CI: 0.77, 0.89]. The GMT ratio (Group 1/Group 2) for the 4 strain-specific influenza HAI titers were H1N1 A/Victoria: 0.95 [95% CI: 0.83, 1.09]; H3N2 A/Darwin: 0.96 [95% CI: 0.85, 1.09]; B/Austria: 0.89 [95% CI: 0.77, 1.04]; B/Phuket: 1.00 [95% CI: 0.89, 1.13].

SARS-CoV-2 Wuhan-Hu-1 strain (Original) neutralizing GMTs were descriptively assessed in a subset of participants, 100 participants from Group 1 and 100 participants from Group 2.

The SARS-CoV-2 neutralization assay (NT50 titer) GMTs increased from baseline to 1 month after vaccination with COMIRNATY from 2,755.9 to 6,773.9 in Group 1 and from 2,421.2 to 7,886.6 in Group 2.

14.2 Children 5 Years Through 11 Years of Age

Efficacy and Immunogenicity of Two-Dose Series (Original Monovalent) in Vaccine-Naïve Children 5 Years Through 11 Years of Age

An efficacy analysis of Study 3 has been performed in 4,051 participants 5 years through 11 years of age without evidence of infection prior to 7 days after Dose 2. This analysis evaluated confirmed symptomatic COVID-19 cases in the placebo-controlled blinded follow-up period accrued up to a data cutoff date of 20 May 2022.

In Study 3, participants 5 years through 11 years of age were enrolled in the United States, Spain, Finland, and Poland. Among participants 5 years through 11 years of age without evidence of prior infection with SARS-CoV-2 through 7 days after Dose 2, who received COMIRNATY (n=2,703) or placebo (n=1,348) in the evaluable efficacy population, 51.2% and 51.0% were male, 48.8% and 49.0% were female, 76.3% and 77.2% were White, 5.5% and 6.0% were Black or African American, 0.5% and 0.3% were American Indian or Alaska Native, 8.9% and 8.5% were Asian, 0.3% and 0% were Native Hawaiian or other Pacific Islander, 8.5% and 7.9% were multiracial or not reported, 15.1% and 15.7% were Hispanic/Latino, 84.8% and 84.3% were non-Hispanic/Latino, and 0.1% and 0% did not report ethnicity, respectively. In the evaluable efficacy population, 25.7% and 25.9% of participants had 1 or more comorbidities that increase the risk of severe COVID-19 disease: defined as participants who had at least 1 of the pre-specified comorbidities based on MMWR 69(32);1081-1088 and/or obesity (BMI ≥95th percentile), respectively. The median age of participants at vaccination was 8.0 years with a range of 5 through 11 years of age in both the COMIRNATY and placebo groups.

The overall vaccine efficacy results and subgroup analysis in participants 5 years through 11 years of age without evidence of prior SARS-CoV-2 infection are presented in Table 23. None of the cases met criteria for severe COVID-19 or multisystem inflammatory syndrome in children (MIS-C).

Table 23: Overall Vaccine Efficacy and Subgroup Analysis [Subgroup analysis was not a prespecified hypothesis, and the results may not necessarily be valid inferences about vaccine efficacy.] – First COVID-19 Occurrence From 7 Days After Dose 2 – Study 3 Participants Without Evidence of Infection Prior to 7 Days After Dose 2 – Evaluable Efficacy Population
First COVID-19 Occurrence From 7 Days after Dose 2 | COMIRNATY; (N [N = number of participants in the specified group.] =2703); Cases; n1 [n1 = Number of participants meeting the endpoint definition.]; Surveillance Time [Total surveillance time in 1000 person-years for the given endpoint across all participants within each group at risk for the endpoint. Time period for COVID-19 case accrual is from 7 days after Dose 2 to the end of the surveillance period.]; (n2 [n2 = Number of participants at risk for the endpoint.]) | Placebo; (N=1348); Cases; n1; Surveillance Time (n2) | Vaccine Efficacy (%); (95% CI [Two-sided 95% confidence interval (CI) for VE is derived based on the Clopper and Pearson method adjusted for surveillance time.])
Overall | 10; 0.591 (2640) | 42; 0.292 (1309) | 88.2; (76.2, 94.7)
Participants with at least one comorbidity of interest [Number of participants who have 1 or more comorbidities that increase the risk of severe COVID-19 disease: defined as participants who had at least one of the prespecified comorbidities based on MMWR Morb Mortal Wkly Rep. 2020;69(32):1081-8 and/or obesity (BMI ≥95th percentile).]
Yes | 2; 0.150 (676) | 13; 0.075 (336) | 92.3; (66.0, 99.2)
No | 8; 0.441 (1964) | 29; 0.217 (973) | 86.4; (69.5, 94.6)
Abbreviations: BMI = body mass index; MMWR = Morbidity and Mortality Weekly Report; NAAT = nucleic acid amplification test; N-binding = SARS-CoV-2 nucleoprotein-binding; SARS-CoV-2 = severe acute respiratory syndrome coronavirus 2.
Note: Participants who had no serological or virological evidence (prior to 7 days after receipt of Dose 2) of past SARS-CoV-2 infection (i.e., N-binding antibody [serum] negative at Dose 1 visit, SARS-CoV-2 not detected by NAAT [nasal swab] at Dose 1 and Dose 2 study visits, and negative NAAT [nasal swab] result at any unscheduled visit prior to 7 days after receipt of Dose 2) and had no medical history of COVID- 19 were included in the analysis.

SARS-CoV-2 50% neutralizing antibody titers (NT50) 1 month after the two-dose series were compared between randomly selected subsets of participants 5 years through 11 years of age from Study 3 (Phase 2/3) and participants 16 years through 25 years of age from efficacy Study 2 (Phase 2/3), using a microneutralization assay against the reference strain (USA_WA1/2020). The primary immunobridging analyses compared the geometric mean titers (using a geometric mean ratio [GMR]) and the seroresponse (defined as achieving at least 4-fold rise in SARS-CoV-2 NT50 from before Dose 1) rate percentages in the evaluable immunogenicity population of participants without evidence of prior SARS-CoV-2 infection up to 1 month after Dose 2 in each group. The pre-specified noninferiority criteria were met for both the GMR and the seroresponse difference (Table 24 and Table 25).

Table 24: SARS-CoV-2 GMTs (NT50) at 1 Month After Primary Series – Immunobridging Subset – Participants 5 Through 11 Years of Age (Study 3) and Participants 16 Through 25 Years of Age (Study 2) – Without Evidence of SARS-CoV-2 Infection up to 1 Month After Dose 2 – Evaluable Immunogenicity Population
 |  | COMIRNATY [Vaccine encoding the viral spike (S) glycoprotein of SARS-CoV-2 Wuhan-Hu-1 strain (Original).] |  | GMT Ratio (95% CI); (5 Through 11 Years of Age / 16 Through 25 Years of Age) [GMT ratio and 2-sided 95% CIs were calculated by exponentiating the mean difference of the logarithms of the titers (5 through 11 years of age minus 16 through 25 years of age) and the corresponding CI (based on the Student t distribution).] , [Noninferiority is declared if the lower bound of the 2-sided 95% CI for the GMT ratio is greater than 0.67 and the point estimate of the GMR is ≥0.8.]
 |  | 5 Through 11 Years of Age; n [n = Number of participants with valid and determinate assay results for the specified assay at the given dose/sampling time point.] =264 | 16 Through 25 Years of Age; n=253 | GMT Ratio (95% CI); (5 Through 11 Years of Age / 16 Through 25 Years of Age) [GMT ratio and 2-sided 95% CIs were calculated by exponentiating the mean difference of the logarithms of the titers (5 through 11 years of age minus 16 through 25 years of age) and the corresponding CI (based on the Student t distribution).] , [Noninferiority is declared if the lower bound of the 2-sided 95% CI for the GMT ratio is greater than 0.67 and the point estimate of the GMR is ≥0.8.]
Assay | Time Point [Protocol-specified timing for blood sample collection.] | GMT [GMTs and 2-sided 95% CIs were calculated by exponentiating the mean logarithm of the titers and the corresponding CIs (based on the Student t distribution). Assay results below the LLOQ were set to 0.5 × LLOQ.]; (95% CI) | GMT; (95% CI) | GMT Ratio (95% CI); (5 Through 11 Years of Age / 16 Through 25 Years of Age) [GMT ratio and 2-sided 95% CIs were calculated by exponentiating the mean difference of the logarithms of the titers (5 through 11 years of age minus 16 through 25 years of age) and the corresponding CI (based on the Student t distribution).] , [Noninferiority is declared if the lower bound of the 2-sided 95% CI for the GMT ratio is greater than 0.67 and the point estimate of the GMR is ≥0.8.]
SARS-CoV-2 neutralization assay − NT50 (titer) [SARS-CoV-2 NT50 were determined using the SARS-CoV-2 mNeonGreen Virus Microneutralization Assay. The assay uses a fluorescent reporter virus derived from the USA_WA1/2020 strain and virus neutralization is read on Vero cell monolayers. The sample NT50 is defined as the reciprocal serum dilution at which 50% of the virus is neutralized.] | 1 month after Dose 2 | 1197.6; (1106.1, 1296.6) | 1146.5; (1045.5, 1257.2) | 1.04; (0.93, 1.18)
Abbreviations: CI = confidence interval; GMR = geometric mean ratio; GMT = geometric mean titer; LLOQ = lower limit of quantitation; NAAT = nucleic acid amplification test; NT50 = 50% neutralizing titer; SARS-CoV-2 = severe acute respiratory syndrome coronavirus 2.
Note: Participants who had no serological or virological evidence (up to 1 month post-Dose 2 blood sample collection) of past SARS-CoV-2 infection (i.e., N-binding antibody [serum] negative at pre-Dose 1 and 1 month after Dose 2, SARS-CoV-2 not detected by NAAT [nasal swab] at pre-Dose 1 and pre-Dose 2, and negative NAAT (nasal swab) at any unscheduled visit up to 1 month after Dose 2 blood collection) and had no medical history of COVID-19 were included in the analysis.

Table 25: Difference in Percentages of Participants With Seroresponse at 1 Month After Primary Series – Immunobridging Subset – Participants 5 Through 11 Years of Age (Study 3) and Participants 16 Through 25 Years of Age (Study 2) Without Evidence of Infection up to 1 Month After Dose 2 – Evaluable Immunogenicity Population
 |  | COMIRNATY [Vaccine encoding the viral spike (S) glycoprotein of SARS-CoV-2 Wuhan-Hu-1 strain (Original).] |  | Difference in Seroresponse Rates % [Difference in proportions, expressed as a percentage (5 through 11 years of age minus 16 through 25 years of age).] (95% CI [2-sided CI, based on the Miettinen and Nurminen method for the difference in proportions, expressed as a percentage.]); (5 Through 11 Years of Age minus 16 Through 25 Years of Age) [Noninferiority is declared if the lower bound of the 2-sided 95% CI for the difference in proportions is greater than -10.0% provided that the immunobridging criteria based on GMR were met.]
 |  | 5 Through 11 Years of Age; N [N = Number of participants with valid and determinate assay results both before vaccination and at 1 month after Dose 2. These values are the denominators for the percentage calculations.] =264 | 16 Through 25 Years of Age; N=253 | Difference in Seroresponse Rates % [Difference in proportions, expressed as a percentage (5 through 11 years of age minus 16 through 25 years of age).] (95% CI [2-sided CI, based on the Miettinen and Nurminen method for the difference in proportions, expressed as a percentage.]); (5 Through 11 Years of Age minus 16 Through 25 Years of Age) [Noninferiority is declared if the lower bound of the 2-sided 95% CI for the difference in proportions is greater than -10.0% provided that the immunobridging criteria based on GMR were met.]
Assay | Time Point [Protocol-specified timing for blood sample collection.] | n [n = Number of participants with seroresponse for the given assay at the given dose/sampling time point.] (%); (95% CI [Exact 2-sided CI based on the Clopper and Pearson method.]) | n (%); (95% CI) | Difference in Seroresponse Rates % [Difference in proportions, expressed as a percentage (5 through 11 years of age minus 16 through 25 years of age).] (95% CI [2-sided CI, based on the Miettinen and Nurminen method for the difference in proportions, expressed as a percentage.]); (5 Through 11 Years of Age minus 16 Through 25 Years of Age) [Noninferiority is declared if the lower bound of the 2-sided 95% CI for the difference in proportions is greater than -10.0% provided that the immunobridging criteria based on GMR were met.]
SARS-CoV-2 neutralization assay − NT50 (titer) [SARS-CoV-2 NT50 were determined using the SARS-CoV-2 mNeonGreen Virus Microneutralization Assay. The assay uses a fluorescent reporter virus derived from the USA_WA1/2020 strain and virus neutralization is read on Vero cell monolayers. The sample NT50 is defined as the reciprocal serum dilution at which 50% of the virus is neutralized.] | 1 month after Dose 2 | 262 (99.2); (97.3, 99.9) | 251 (99.2); (97.2, 99.9) | 0.0; (-2.0, 2.2)
Abbreviations: CI = confidence interval; GMR = geometric mean ratio; LLOQ = lower limit of quantitation; NAAT = nucleic acid amplification test; N-binding = SARS-CoV-2 nucleoprotein–binding; NT50 = 50% neutralizing titer 50; SARS-CoV-2 = severe acute respiratory syndrome coronavirus 2.
Note: Seroresponse is defined as achieving a ≥4-fold rise from baseline (before Dose 1). If the baseline measurement is below the LLOQ, a post-vaccination assay result ≥4 × LLOQ is considered a seroresponse.
Note: Participants who had no serological or virological evidence (up to 1 month post-Dose 2 blood sample collection) of past SARS-CoV-2 infection (i.e., N-binding antibody [serum] negative at pre-Dose 1 and 1 month after Dose 2, SARS-CoV-2 not detected by NAAT [nasal swab] at pre-Dose 1 and pre-Dose 2, and negative NAAT (nasal swab) at any unscheduled visit up to 1 month after Dose 2 blood collection) and had no medical history of COVID-19 were included in the analysis.

Immunogenicity of a Single Dose (Original Monovalent) in Vaccine-Experienced Children 5 Years Through 11 Years of Age

In Study 3, immunogenicity of a first booster dose of COMIRNATY administered after the second dose of the two-dose series with COMIRNATY was evaluated in 67 study participants 5 through 11 years of age who had no serological or virological evidence of past SARS-CoV-2 infection up to 1 month after the booster dose. Using a microneutralization assay against the reference strain of SARS-CoV-2 (USA_WA1/2020), the NT50 GMT at 1 month after the booster dose (2,720.9 [95% CI: 2,280.1, 3,247.0]) was increased compared to before the booster dose (271.0 [95% CI: 229.1, 320.6]).

Immunogenicity of a Single Dose (Monovalent XBB.1.5) in Vaccine-Naïve Children 5 Years Through 11 Years of Age

In an analysis of a subset of Study 6, immunogenicity of a single dose of COMIRNATY (encoding the viral spike (S) glycoprotein of SARS-CoV-2 Omicron XBB.1.5) in COVID-19 vaccine-naïve participants 5 through 11 years of age (n=285) was compared to participants 12 years of age and older who had received at least 3 prior U.S.-authorized mRNA COVID-19 vaccine doses and then received a single dose of COMIRNATY (encoding the viral spike (S) glycoprotein of SARS-CoV-2 Omicron XBB.1.5, 30 mcg of modRNA) in a subset of study C4591054 (Study 13; NCT 05997290) (n=302). Study 13 evaluated safety and immunogenicity of a single dose of COMIRNATY administered to COVID-19 vaccine-experienced participants 12 years of age and older. In Study 6 and Study 13, 98.9% and 99.3% of participants had evidence of prior SARS-CoV-2 infection at baseline, respectively.

Study 6 was conducted in Brazil, Puerto Rico, South Africa and United States. Among the COVID-19 vaccine−naïve participants 5 through 11 years of age in Study 6 (n=285) and COVID-19 vaccine-experienced participants 12 years of age and older in Study 13 (n=302) who received a single dose of COMIRNATY in the evaluable immunogenicity population, 46.3% and 41.7% were male, 53.7% and 58.3% were female, 41.1% and 79.1% were White, 53.0% and 12.9% were Black or African American, 0.4% and 0% were American Indian or Alaska Native, 2.1% and 5.0% were Asian, 0% and 0.3% were Native Hawaiian or other Pacific Islander, 3.5% and 2.6% were multiracial, not reported, or unknown, 53.3% and 19.2% were Hispanic/Latino, and 46.7% and 80.1% were non-Hispanic/Latino, respectively. At study vaccination, the median age of participants in Study 6 was 7.0 years (range 5 through 11 years of age) and the median age of participants in Study 13 was 53.5 years (range 12 through 82 years).

The primary immunobridging analyses compared the geometric mean titers (using a geometric mean ratio [GMR]) and the seroresponse (defined as achieving at least 4-fold rise from baseline) rates in the COVID-19 vaccine-naïve participants 5 through 11 years of age to COVID-19 vaccine-experienced participants 12 years of age and older. The noninferiority criteria were met for both the GMR and the seroresponse rate percentages (Table 26 and Table 27).

Table 26: Geometric Mean Ratio – Study 6 to Study 13 – Participants at 1 Month After Study Vaccination – Evaluable Immunogenicity Population
 | Study 6; COVID-19 Vaccine-Naïve; 5 Through 11 Years of Age; COMIRNATY [Vaccine encoding the viral spike (S) glycoprotein of SARS-CoV-2 Omicron XBB.1.5.] |  | Study 13; COVID-19 Vaccine-Experienced; ≥12 Years of Age; COMIRNATY |  | Study 6/Study 13
SARS-CoV-2 Neutralization Assay | n [n = Number of participants with valid and determinate assay results for the specified assay at the given sampling time point.] | GMT [GMTs and 2-sided 95% CIs were calculated by exponentiating the mean logarithm of the titers and the corresponding CIs (based on the Student t distribution). Assay results below the LLOQ were set to 0.5 × LLOQ.]; (95% CI) | n | GMT; (95% CI) | GMR [GMRs and 2-sided 95% CIs were calculated by exponentiating the difference of LS Means for the assay (Study 6, 5 through 11 years of age – Study 13, 12 years of age and older) and the corresponding CIs based on a linear regression model with baseline log-transformed neutralizing titers, postbaseline infection status, and vaccine group as covariates.]; (95% CI)
Omicron XBB.1.5 - NT50 (titer) [SARS-CoV-2 NT50 were determined using a validated 384-well assay platform (Omicron subvariant XBB.1.5).] | 285 | 5930.5; (5283.8, 6656.4) | 302 | 4006.4; (3438.3, 4668.4) | 1.81; (1.51, 2.16) [Noninferiority is declared if the lower bound of the 2-sided 95% CI for the GMR is greater than 0.67 and the point estimate of the GMR is ≥0.8.]
Abbreviations: CI = confidence interval; GMR = geometric mean ratio; GMT = geometric mean titer; LLOQ = lower limit of quantitation; LS = least square; NT50 = 50% neutralizing titer; SARS-CoV-2 = severe acute respiratory syndrome coronavirus 2.

Table 27: Difference in Percentages of Participants With Seroresponse Between Study 6 and Study 13 Participants at 1 Month After the Study Vaccination – Evaluable Immunogenicity Population
 | Study 6; COVID-19 Vaccine-Naïve; 5 Through 11 Years of Age COMIRNATY [Vaccine encoding the viral spike (S) glycoprotein of SARS-CoV-2 Omicron XBB.1.5.] |  | Study 13; COVID-19 Vaccine-Experienced; ≥12 Years of Age COMIRNATY |  | Difference
SARS-CoV-2 Neutralization Assay | N [N = Number of participants with valid and determinate assay results for the specified assay both before vaccination and at the given sampling time point. This value is the denominator for the percentage calculations.] | n [n = Number of participants with seroresponse for the given assay at the given sampling time point.] (%); (95% CI [Exact 2-sided 95% CI based on the Clopper and Pearson method.]) | N | n (%); (95% CI) | % [Adjusted difference in proportions based on the Miettinen and Nurminen method stratified by baseline neutralizing titer category (< median, ≥ median), expressed as a percentage (Study 6, 5 through 11 years of age – Study 13, 12 years of age and older). The median of baseline neutralizing titers was calculated based on the pooled data in 2 comparator groups.] | 95% CI [2-sided 95% CI, based on the Miettinen and Nurminen method for the difference in proportions stratified by baseline neutralizing titer category (< median, ≥ median), expressed as a percentage.]
Omicron XBB.1.5 - NT50 (titer) [SARS-CoV-2 NT50 were determined using a validated 384-well assay platform (Omicron subvariant XBB.1.5).] | 285 | 253 (88.8); (84.5, 92.2) | 300 | 231 (77.0); (71.8, 81.6) | 8.97 | (3.91, 14.02) [Noninferiority is declared if the lower bound of the 2-sided 95% CI for the adjusted difference in percentage of participants with seroresponse is greater than -10.0%.]
Abbreviations: CI = confidence interval; LLOQ = lower limit of quantitation; NT50 = 50% neutralizing titer; SARS-CoV-2 = severe acute respiratory syndrome coronavirus 2.
Note: Seroresponse is defined as achieving a ≥4-fold rise from baseline. If the baseline measurement is below the LLOQ, a post-vaccination assay result ≥4 × LLOQ is considered a seroresponse.

15 REFERENCES

1. Jain SS, Anderson SA, Steele JM, et al. Cardiac manifestations and outcomes of COVID-19 vaccine-associated myocarditis in the young in the USA: longitudinal results from the Myocarditis After COVID Vaccination (MACiV) multicenter study. Lancet. 2024;76:1-13. https://doi.org/10.1016/j.eclinm.2024.102809

16 HOW SUPPLIED/STORAGE AND HANDLING

COMIRNATY is supplied as follows:

- COMIRNATY Single-Dose Prefilled Syringes for Individuals 65 Years of Age and Older and Individuals 12 Years Through 64 Years of Age with at Least One Underlying Condition that Puts Them at High Risk for Severe Outcomes from COVID-19:
  - Carton of 10 single-dose prefilled syringes: NDC 0069-2528-10
  - Single-dose prefilled syringe: NDC 0069-2528-01
  - Supplied in prefilled syringes labeled with gray borders
- COMIRNATY Single-Dose Vials for Individuals 5 Through 11 Years of Age with at Least One Underlying Condition that Puts Them at High Risk for Severe Outcomes from COVID-19:
  - Carton of 10 single-dose vials: NDC 0069-2501-10
  - Single-dose vial: NDC 0069-2501-01
  - Supplied in vials with blue caps and labeled with blue borders

STORAGE AND HANDLING

During storage, minimize exposure to room light, and avoid exposure to direct sunlight and ultraviolet light.

Do not use the vaccine after the expiration date printed on the vials, prefilled syringes, and cartons.

Storage Prior to Use

Prefilled Syringes

Store COMIRNATY prefilled syringes refrigerated at 2°C to 8°C (35°F to 46°F). DO NOT FREEZE.

The total time out of refrigeration (at temperatures between 8°C and 25°C (46°F and 77°F)) must not exceed 12 hours.

Single-Dose Vials

COMIRNATY single-dose vials may arrive frozen at ultra-cold conditions in thermal containers with dry ice. Once received, frozen vials may be immediately transferred to the refrigerator at 2ºC to 8ºC (35ºF to 46ºF), thawed and stored for up to 10 weeks. The 10-week refrigerated expiry date should be recorded on the carton at the time of transfer. Cartons of 10 single-dose vials may take up to 2 hours to thaw at this temperature. Once thawed, they should not be refrozen.

Alternatively, single-dose vials may be stored in an ultra-low temperature freezer at -90ºC to -60ºC (-130ºF to -76ºF). Do not store vials at -25°C to -15°C (-13°F to 5°F).

Cartons of COMIRNATY single-dose vials may be received at 2°C to 8°C (35ºF to 46ºF), and they should be stored at 2°C to 8°C (35ºF to 46ºF). Check that the carton has been previously updated to reflect the 10-week refrigerated expiry date.

The total time out of refrigeration (at temperatures between 8°C and 25°C (46°F and 77°F)) must not exceed 12 hours.

17 PATIENT COUNSELING INFORMATION

Advise the vaccine recipient or caregiver to read the FDA-approved patient labeling.

Inform the vaccine recipient or caregiver of the potential benefits and risks of vaccination with COMIRNATY.

Advise the vaccine recipient or caregiver to report any adverse events to their healthcare provider or to the Vaccine Adverse Event Reporting System at 1-800-822-7967 and www.vaers.hhs.gov.

This product’s labeling may have been updated. For the most recent prescribing information, please visit https://dailymed.nlm.nih.gov/dailymed/.

Manufactured for
BioNTech Manufacturing GmbH
An der Goldgrube 12
55131 Mainz, Germany

Manufactured by
Pfizer Inc., New York, NY 10001

LAB-1490-15.0

US Govt. License No. 2229

Patient Package Insert

INFORMATION FOR RECIPIENTS AND CAREGIVERS

COMIRNATY (Cuh-mir'-na-tee)

(COVID-19 VACCINE, mRNA)

(2025-2026 Formula)

This summary is not intended to take the place of talking with your or your child’s healthcare provider. If you have questions or would like more information, please talk with the healthcare provider.

What is COMIRNATY?

COMIRNATY is a vaccine to protect against COVID-19. COMIRNATY is for people who are:

- 65 years of age and older, or
- 5 years through 64 years of age at high risk for severe COVID-19.

Vaccination with COMIRNATY may not protect all people who receive the vaccine.

COMIRNATY does not contain SARS-CoV-2, the virus that causes COVID-19. COMIRNATY cannot give you or your child COVID-19.

Who should not get COMIRNATY?

You or your child should not get COMIRNATY if you or your child had:

- a severe allergic reaction after a previous dose of COMIRNATY or any Pfizer-BioNTech COVID-19 vaccine
- a severe allergic reaction to any ingredient in these vaccines (see What are the ingredients in COMIRNATY?).

Before getting COMIRNATY, tell the vaccination provider about all of your or your child’s medical conditions, including if you or your child:

- have any allergies
- had a severe allergic reaction after receiving a previous dose of any COVID-19 vaccine
- have had myocarditis (inflammation of the heart muscle) or pericarditis (inflammation of the lining outside the heart)
- have a fever
- have a bleeding disorder or are on a blood thinner
- are immunocompromised or are on a medicine that affects the immune system
- are pregnant or plan to become pregnant
- are breastfeeding
- have received another COVID-19 vaccine
- have ever fainted in association with an injection

How is COMIRNATY given?

COMIRNATY is given as an injection into the muscle.

What are the risks of COMIRNATY?

There is a remote chance that COMIRNATY could cause a severe allergic reaction. A severe allergic reaction would usually occur within a few minutes to 1 hour after getting a dose. For this reason, the vaccination provider may ask you or your child to stay at the place where you or your child received the vaccine for monitoring after vaccination. Signs of a severe allergic reaction can include:

- Difficulty breathing
- Swelling of the face and throat
- A fast heartbeat
- A bad rash all over the body
- Dizziness and weakness

Myocarditis (inflammation of the heart muscle) and pericarditis (inflammation of the lining outside the heart) have occurred in some people who have received mRNA COVID-19 vaccines, including COMIRNATY and Pfizer-BioNTech COVID-19 vaccines. Myocarditis and pericarditis following administration of mRNA COVID-19 vaccines have occurred most commonly in males 12 years through 24 years of age. In most of these people, symptoms began within a week following vaccination. Based on available data, estimated rates of myocarditis and/or pericarditis from 1 through 7 days after getting a dose of the 2023-2024 Formula of mRNA COVID-19 vaccines were approximately 8 cases per million doses in people 6 months through 64 years of age and approximately 27 cases per million doses in males 12 years through 24 years of age.

In most people who have had myocarditis or pericarditis after receiving an mRNA COVID-19 vaccine, symptoms have gone away a few days after receiving treatment with medicines used to reduce inflammation.

In a study, follow-up information was collected on people who developed myocarditis after receiving the original formula of a COVID-19 vaccine; most people had received an mRNA COVID-19 vaccine. Some people in the study reported having heart symptoms approximately 3 months after developing myocarditis. Some people in the study had heart MRIs (scans that show detailed images of the heart muscle) initially after developing myocarditis and again approximately 5 months later. The initial and follow-up heart MRIs commonly showed signs of injury to the heart muscle, with improvement over time in most people. It is not known if these heart MRI findings might predict long-term heart effects of myocarditis. Studies are underway to find out if there are long-term heart effects in people who have had myocarditis after receiving an mRNA COVID-19 vaccine.

You should seek medical attention right away if you or your child have any of the following symptoms after receiving COMIRNATY, particularly during the 2 weeks after receiving a dose of the vaccine:

- Chest pain
- Shortness of breath
- Feelings of having a fast-beating, fluttering, or pounding heart

These could be symptoms of myocarditis or pericarditis.

Additional symptoms, particularly in children, may include:

- Fainting
- Unusual and persistent fatigue or lack of energy
- Persistent vomiting
- Persistent pain in the abdomen
- Unusual and persistent cool, pale skin

Side effects that have been reported with COMIRNATY or Pfizer-BioNTech COVID-19 vaccines include:

- Severe allergic reactions
- Non-severe allergic reactions such as rash, itching, hives, or swelling of the face
- Myocarditis (inflammation of the heart muscle)
- Pericarditis (inflammation of the lining outside the heart)
- Injection site reactions: pain, swelling, redness, arm pain
- General side effects: tiredness, headache, muscle pain, chills, joint pain, fever, nausea, feeling unwell, swollen lymph nodes (lymphadenopathy), decreased appetite, diarrhea, vomiting, dizziness
- Fainting in association with injection of the vaccine
- Febrile seizures (convulsions during a fever) in children 5 through 11 years of age

These may not be all the possible side effects of COMIRNATY. Ask your or your child’s healthcare provider about any side effects that concern you.

Report vaccine side effects to FDA/CDC Vaccine Adverse Event Reporting System (VAERS). The VAERS toll-free number is 1-800-822-7967 or report online to https://vaers.hhs.gov/reportevent.html.

In addition, you can report side effects to Pfizer Inc. at 1-800-438-1985 or www.pfizersafetyreporting.com.

What if you or your child are pregnant or breastfeeding?

If you or your child are pregnant or breastfeeding, discuss your options with the healthcare provider.

What are the ingredients in COMIRNATY?

COMIRNATY contains the following ingredients:

- messenger ribonucleic acid (mRNA)
- lipids (((4-hydroxybutyl)azanediyl)bis(hexane-6,1-diyl)bis(2-hexyldecanoate), 2-(polyethylene glycol 2000)-N,N-ditetradecylacetamide, 1,2-distearoyl-sn-glycero-3-phosphocholine, and cholesterol)
- tromethamine
- tromethamine hydrochloride
- sucrose

COMIRNATY does not contain preservatives.

This Information for Recipients and Caregivers may have been updated. For the most recent Information for Recipients and Caregivers, please visit https://dailymed.nlm.nih.gov/dailymed/.

If you have questions, talk to your healthcare provider or visit www.COMIRNATY.com or call 1-877-VAX-CO19 (1-877-829-2619).

Manufactured for
BioNTech Manufacturing GmbH
An der Goldgrube 12
55131 Mainz, Germany

Manufactured by
Pfizer Inc., New York, NY 10001

LAB-1587-7.0

US Govt. License No. 2229

Revised: 8/2025

PRINCIPAL DISPLAY PANEL - Glass Prefilled Syringe Label 2025-2026 Formula

NDC 0069-2528-01
Rx only

COVID-19 Vaccine, mRNA
COMIRNATY®

2025 – 2026 Formula

DO NOT FREEZE

1 dose of 0.3 mL

For intramuscular use.
US License No. 2229
BioNTech Manufacturing
GmbH & Pfizer Inc.

PRINCIPAL DISPLAY PANEL - Glass Prefilled Syringe Carton 2025-2026 Formula

NDC 0069-2528-10

COVID-19 Vaccine, mRNA
COMIRNATY®

2025 – 2026 Formula

Injectable Suspension, for Intramuscular Use

10 Single-Dose Prefilled Syringes

Each prefilled syringe contains 1 dose of 0.3 mL

For 12 years through 64 years of age at
high-risk for severe COVID-19
For 65 years of age and older

DO NOT FREEZE

BIONTECH
Pfizer
Rx only

PRINCIPAL DISPLAY PANEL - Glass Single-Dose Vial Label 2025-2026 Formula

COVID-19 Vaccine, mRNA
COMIRNATY®
Rx only

2025 – 2026 Formula

DO NOT DILUTE

Vial contains 1 dose of 0.3 mL

For intramuscular use.
US License No. 2229
BioNTech Manufacturing GmbH & Pfizer Inc.

NDC 0069-2501-01

PRINCIPAL DISPLAY PANEL - Glass Single-Dose Vial Carton 2025-2026 Formula

NDC 0069-2501-10

COVID-19 Vaccine, mRNA
COMIRNATY®

2025 – 2026 Formula

Injectable Suspension, for Intramuscular Use

DO NOT DILUTE

10 Single-Dose Vials

Each vial contains 1 dose of 0.3 mL

For 5 years through 11 years of age at high-risk for severe COVID-19

BIONTECH
Pfizer
Rx only